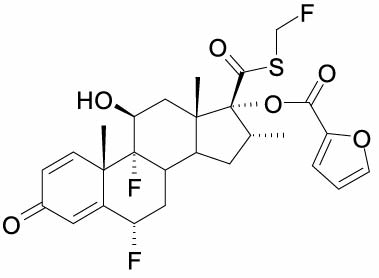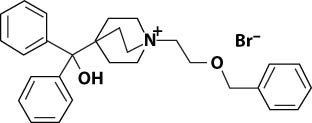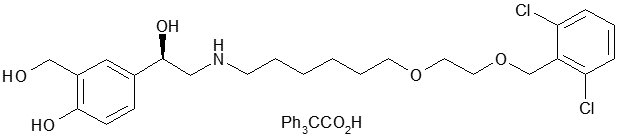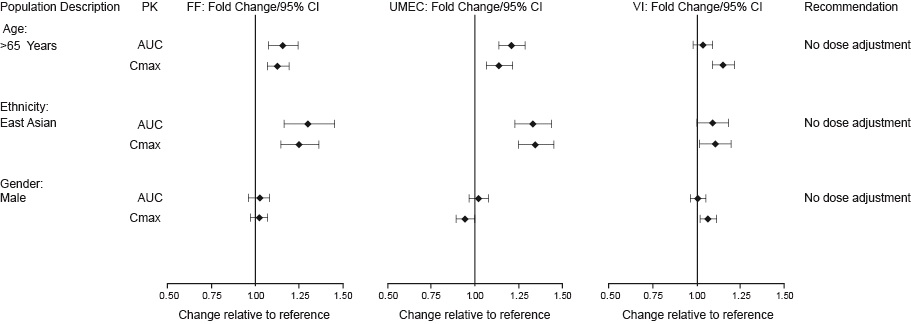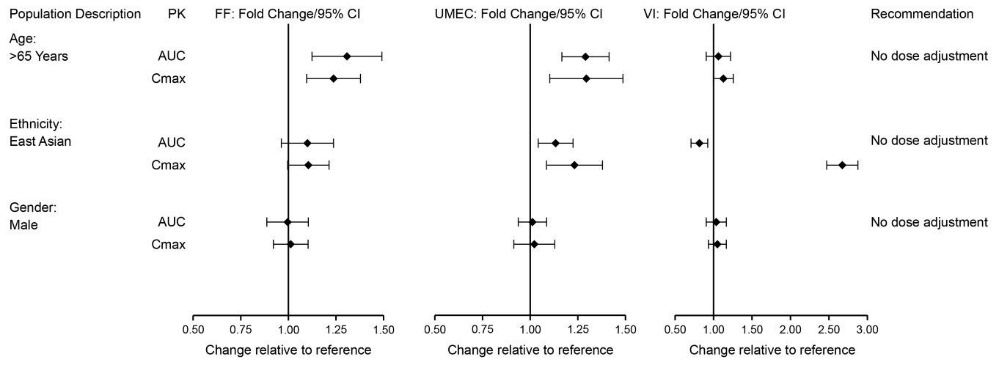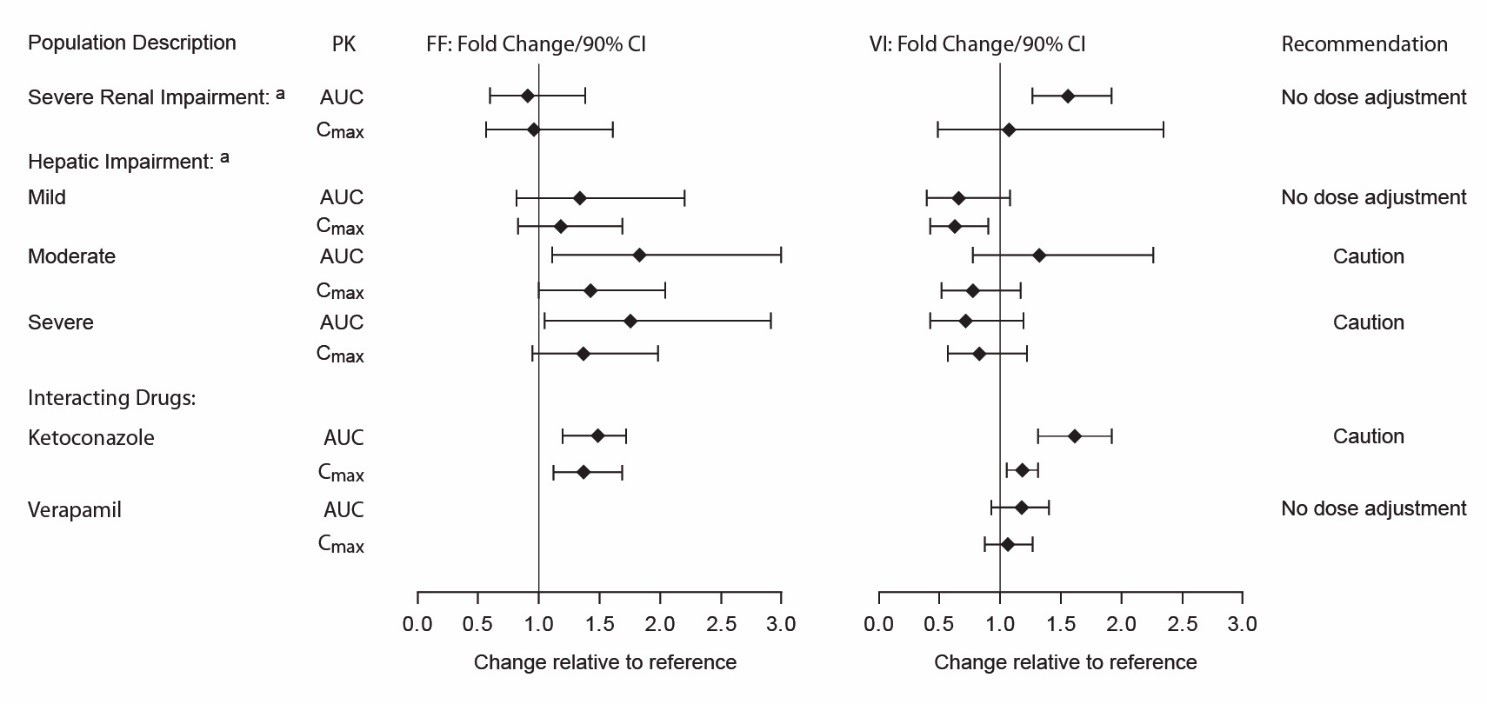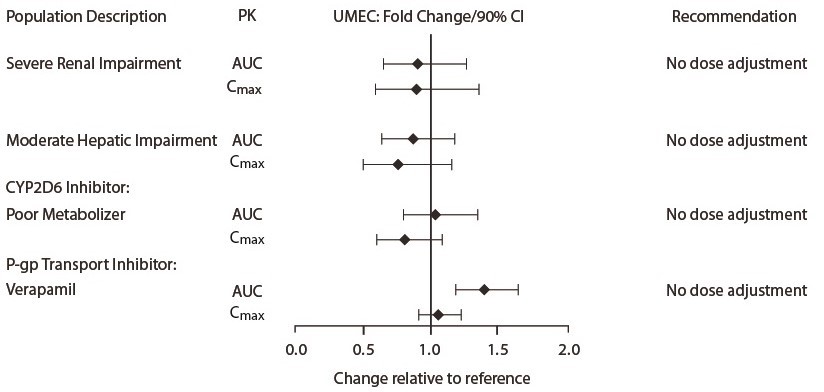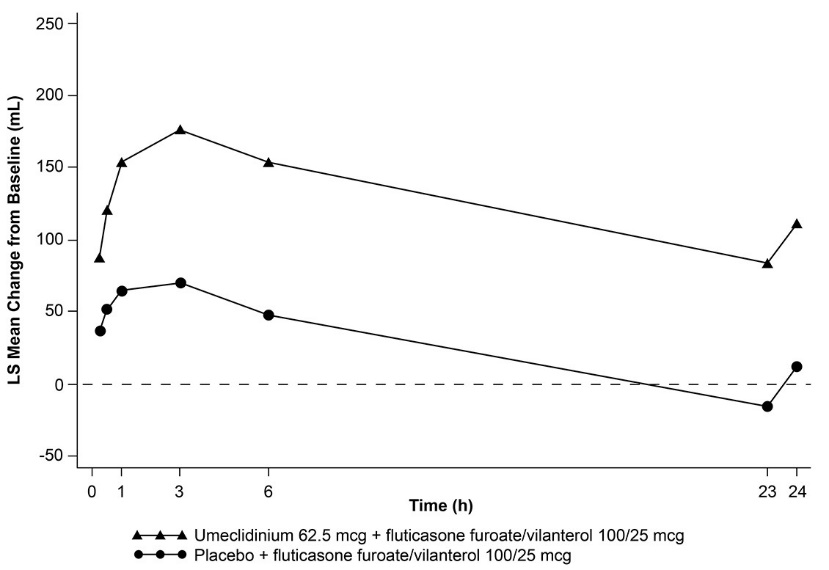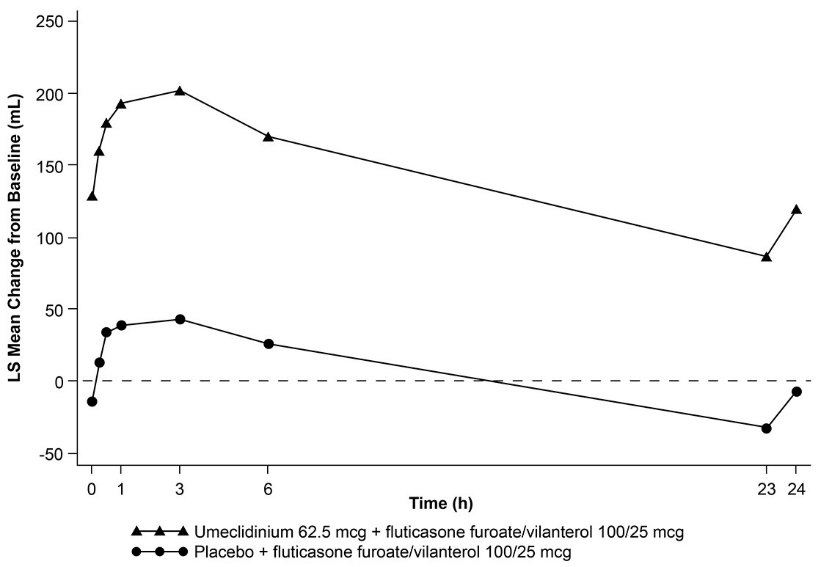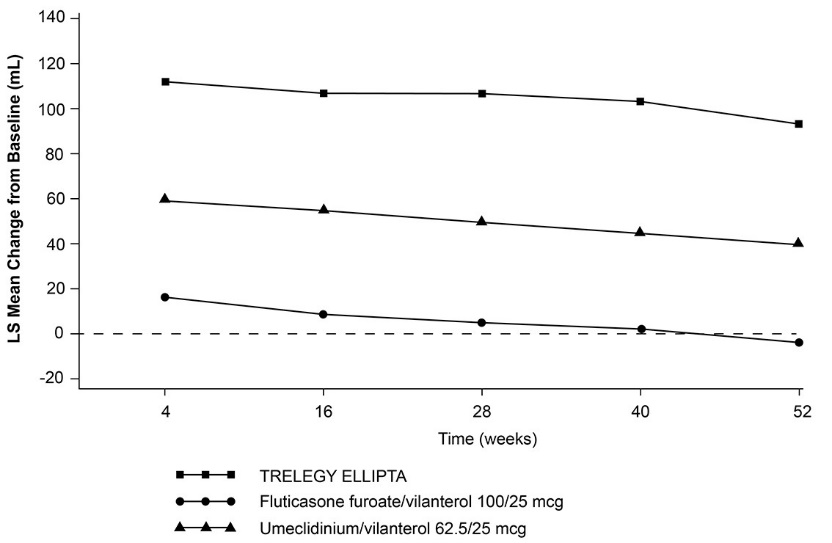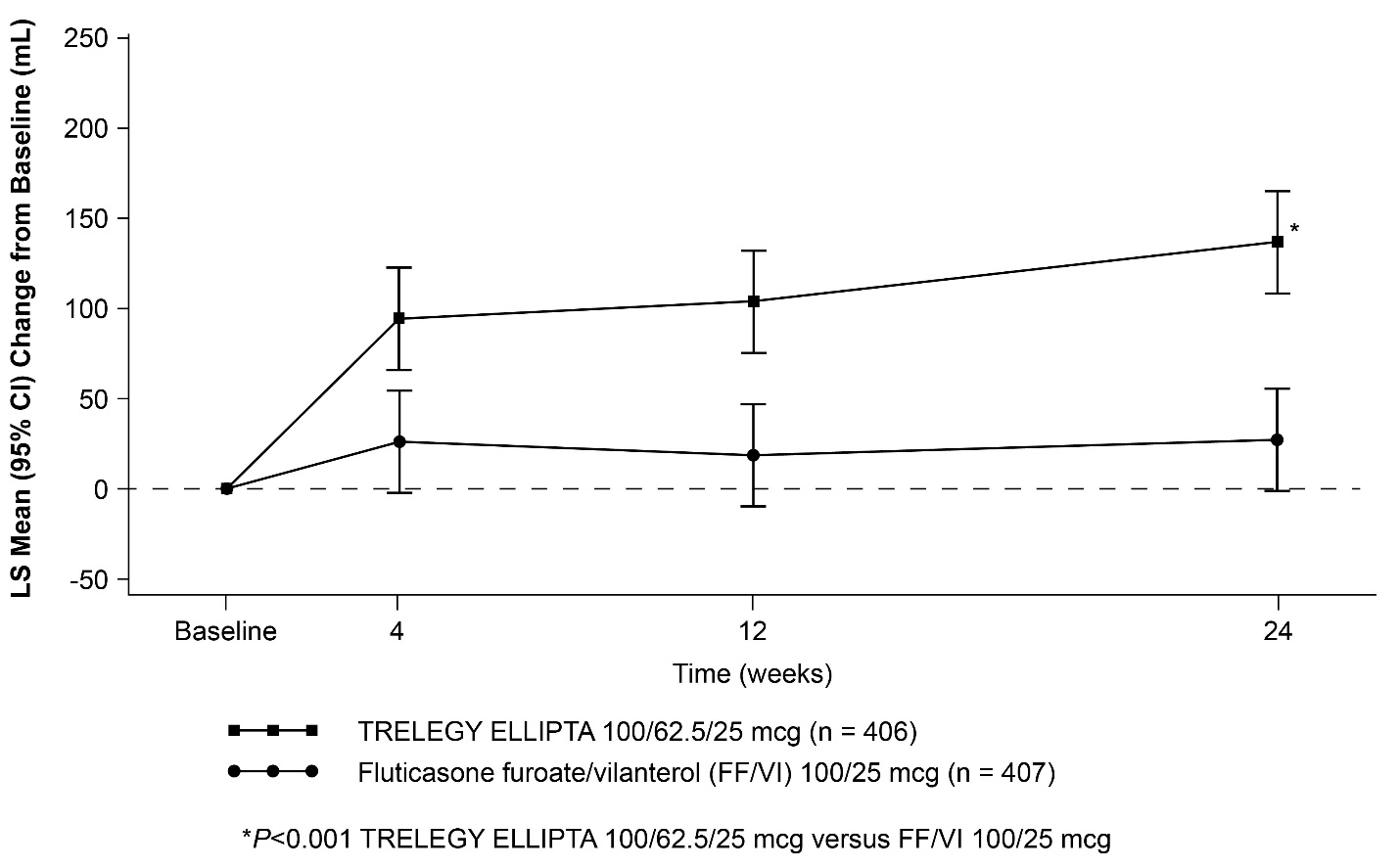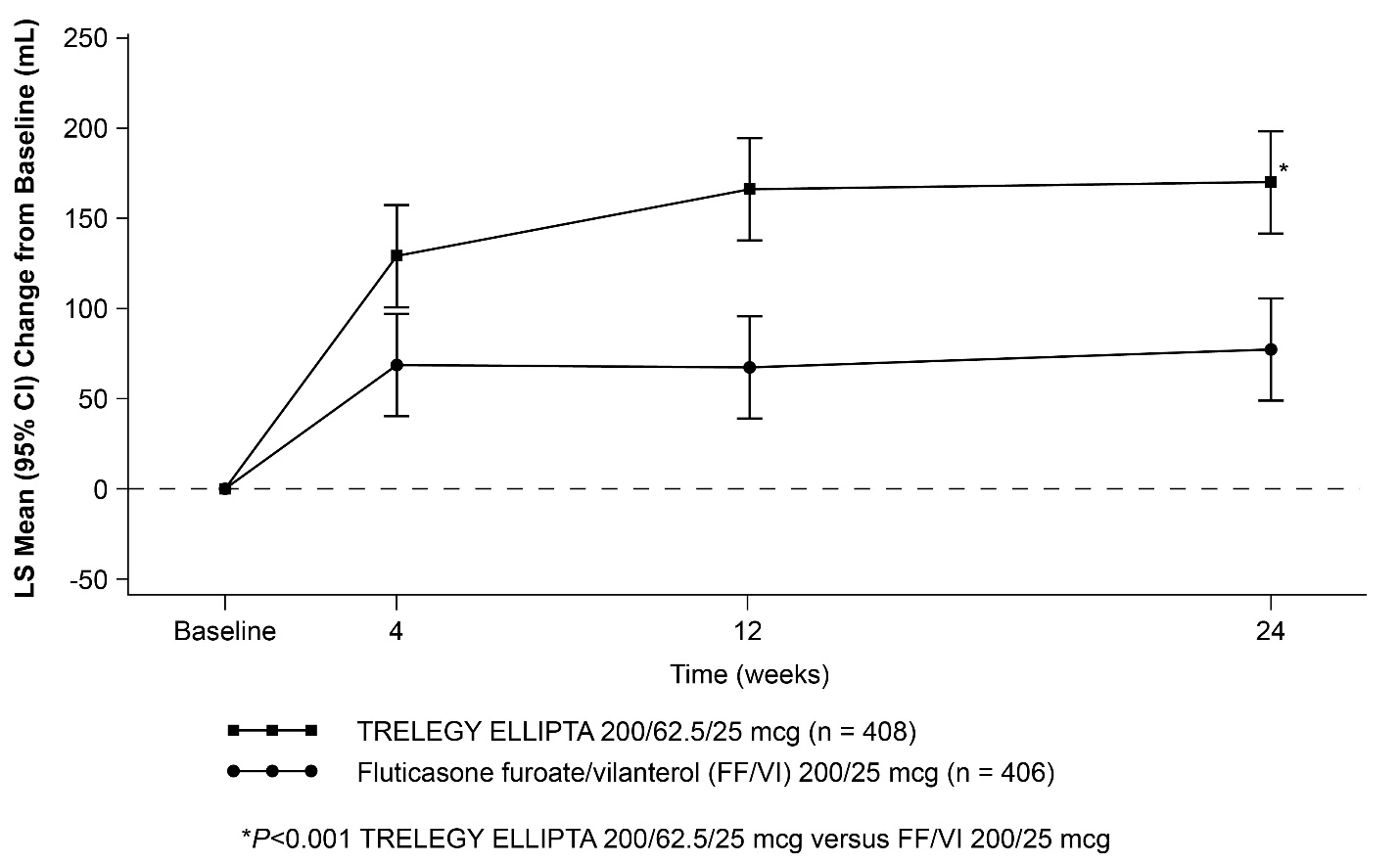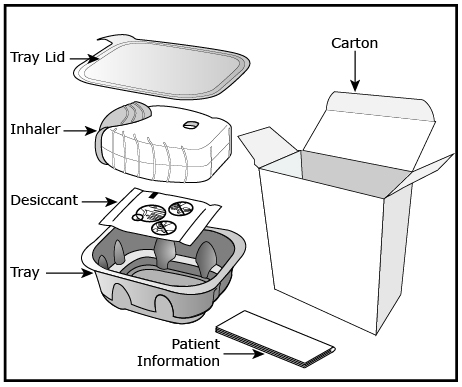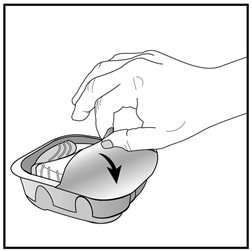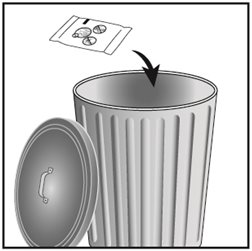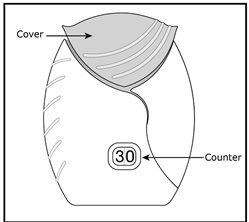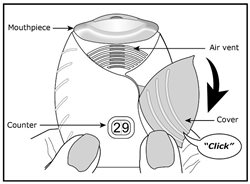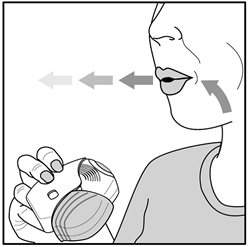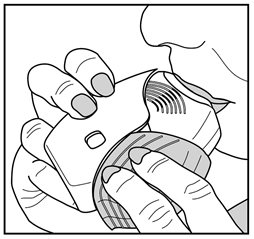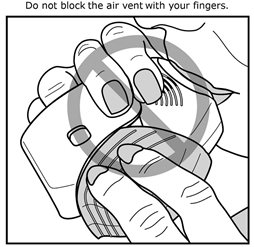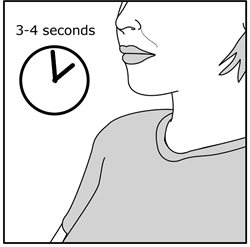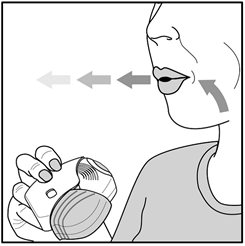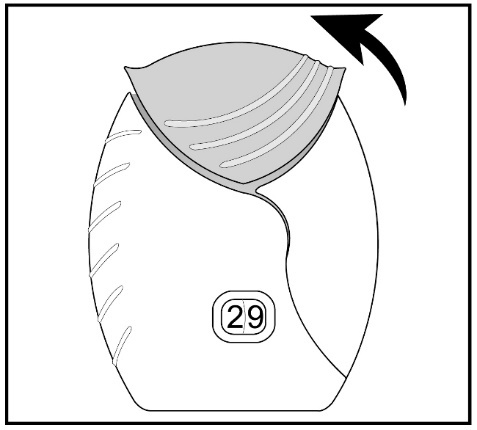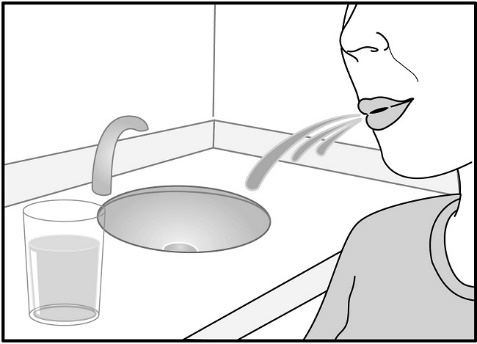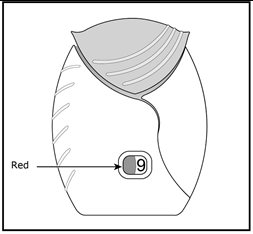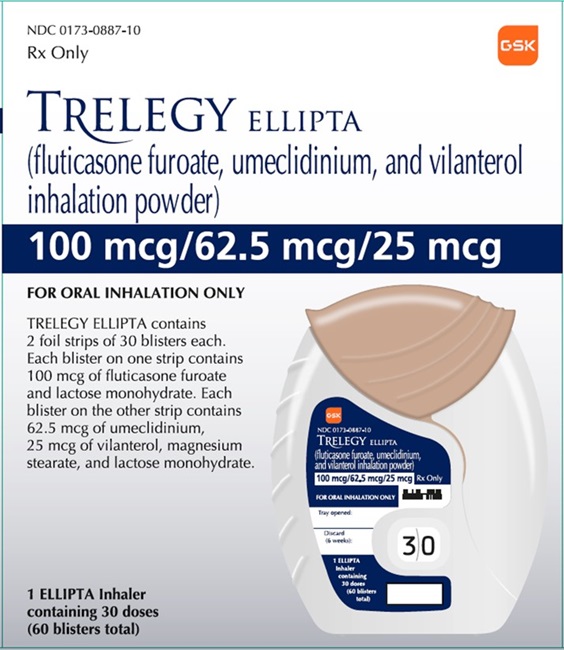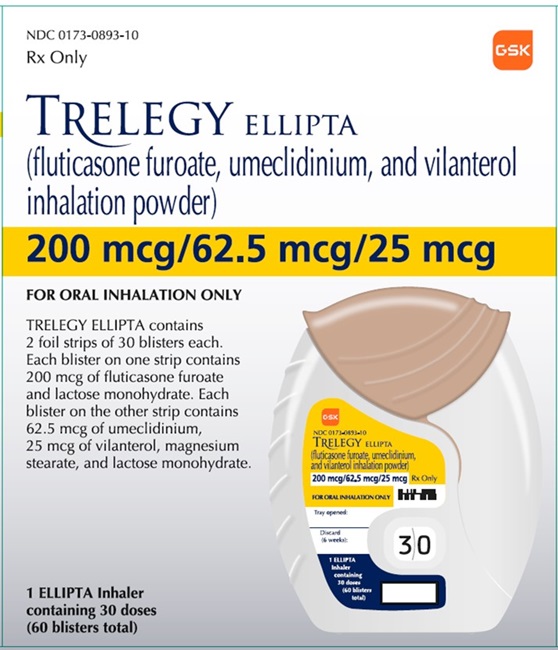 DRUG LABEL: Trelegy Ellipta
NDC: 0173-0887 | Form: POWDER
Manufacturer: GlaxoSmithKline LLC
Category: prescription | Type: HUMAN PRESCRIPTION DRUG LABEL
Date: 20230602

ACTIVE INGREDIENTS: FLUTICASONE FUROATE 100 ug/1 1; UMECLIDINIUM BROMIDE 62.5 ug/1 1; VILANTEROL TRIFENATATE 25 ug/1 1
INACTIVE INGREDIENTS: MAGNESIUM STEARATE; LACTOSE MONOHYDRATE

HIGHLIGHTS OF PRESCRIBING INFORMATION

These highlights do not include all the information needed to use TRELEGY ELLIPTA safely and effectively. See full prescribing information for TRELEGY ELLIPTA.
TRELEGY ELLIPTA (fluticasone furoate, umeclidinium, and vilanterol inhalation powder), for oral inhalation use
Initial U.S. Approval: 2017

1 INDICATIONS AND USAGE

TRELEGY ELLIPTA is a combination of fluticasone furoate, an inhaled corticosteroid (ICS); umeclidinium, an anticholinergic; and vilanterol, a long-acting beta2-adrenergic agonist (LABA), indicated for:

- the maintenance treatment of patients with chronic obstructive pulmonary disease (COPD). (1.1)
- the maintenance treatment of asthma in patients aged 18 years and older. (1.2)

Limitations of Use: Not indicated for relief of acute bronchospasm. (1.3, 5.2)

2 DOSAGE AND ADMINISTRATION

- For oral inhalation only. (2.1)
- Maintenance treatment of COPD: 1 actuation of TRELEGY ELLIPTA 100/62.5/25 mcg once daily administered by oral inhalation. (2.2)
- Maintenance treatment of asthma: 1 actuation of TRELEGY ELLIPTA 100/62.5/25 mcg or TRELEGY ELLIPTA 200/62.5/25 mcg once daily administered by oral inhalation. (2.3)

3 DOSAGE FORMS AND STRENGTHS

Inhalation powder:

- 100 mcg fluticasone furoate, 62.5 mcg umeclidinium, and 25 mcg vilanterol (100/62.5/25 mcg) per actuation. (3)
- 200 mcg fluticasone furoate, 62.5 mcg umeclidinium, and 25 mcg vilanterol (200/62.5/25 mcg) per actuation. (3)

4 CONTRAINDICATIONS

- Primary treatment of status asthmaticus or acute episodes of COPD or asthma requiring intensive measures. (4)
- Severe hypersensitivity to milk proteins or any ingredients. (4)

5 WARNINGS AND PRECAUTIONS

- LABA monotherapy increases the risk of serious asthma-related events. (5.1)
- Do not initiate in acutely deteriorating COPD or asthma. Do not use to treat acute symptoms. (5.2)
- Do not use in combination with additional therapy containing a LABA because of risk of overdose. (5.3)
- Candida albicans infection of the mouth and pharynx may occur. Monitor patients periodically. Advise the patient to rinse his/her mouth with water without swallowing after inhalation to help reduce the risk. (5.4)
- Increased risk of pneumonia in patients with COPD. Monitor patients for signs and symptoms of pneumonia. (5.5)
- Potential worsening of infections (e.g., existing tuberculosis; fungal, bacterial, viral, or parasitic infections; ocular herpes simplex). Use with caution in patients with these infections. More serious or even fatal course of chickenpox or measles can occur in susceptible patients. (5.6)
- Risk of impaired adrenal function when transferring from systemic corticosteroids. Wean patients slowly from systemic corticosteroids if transferring to TRELEGY ELLIPTA. (5.7)
- Hypercorticism and adrenal suppression may occur with very high dosages or at the regular dosage in susceptible individuals. If such changes occur, discontinue TRELEGY ELLIPTA slowly. (5.8)
- If paradoxical bronchospasm occurs, discontinue TRELEGY ELLIPTA and institute alternative therapy. (5.10)
- Use with caution in patients with cardiovascular disorders because of beta-adrenergic stimulation. (5.12)
- Assess for decrease in bone mineral density initially and periodically thereafter. (5.13)
- Glaucoma and cataracts may occur with long-term use of ICS. Worsening of narrow-angle glaucoma may occur. Use with caution in patients with narrow-angle glaucoma and instruct patients to contact a healthcare provider immediately if symptoms occur. Consider referral to an ophthalmologist in patients who develop ocular symptoms or use TRELEGY ELLIPTA long term. (5.14)
- Worsening of urinary retention may occur. Use with caution in patients with prostatic hyperplasia or bladder-neck obstruction and instruct patients to contact a healthcare provider immediately if symptoms occur. (5.15)
- Use with caution in patients with convulsive disorders, thyrotoxicosis, diabetes mellitus, and ketoacidosis. (5.16)
- Be alert to hypokalemia and hyperglycemia. (5.17)

6 ADVERSE REACTIONS

- COPD: Most common adverse reactions (incidence ≥1%) are upper respiratory tract infection, pneumonia, bronchitis, oral candidiasis, headache, back pain, arthralgia, influenza, sinusitis, pharyngitis, rhinitis, dysgeusia, constipation, urinary tract infection, diarrhea, gastroenteritis, oropharyngeal pain, cough, and dysphonia. (6.1)
- Asthma: Most common adverse reactions (incidence ≥2%) are pharyngitis/nasopharyngitis, upper respiratory tract infection/viral upper respiratory tract infection, bronchitis, respiratory tract infection/viral respiratory tract infection, sinusitis/acute sinusitis, urinary tract infection, rhinitis, influenza, headache, and back pain. (6.2)

To report SUSPECTED ADVERSE REACTIONS, contact GlaxoSmithKline at 1-888-825-5249 or FDA at 1-800-FDA-1088 or www.fda.gov/medwatch.

7 DRUG INTERACTIONS

- Strong cytochrome P450 3A4 inhibitors (e.g., ketoconazole): Use with caution. May cause systemic corticosteroid and cardiovascular effects. (7.1)
- Monoamine oxidase inhibitors and tricyclic antidepressants: Use with extreme caution. May potentiate effect of vilanterol on cardiovascular system. (7.2)
- Beta-blockers: Use with caution. May block bronchodilatory effects of beta-agonists and produce severe bronchospasm. (7.3)
- Diuretics: Use with caution. Electrocardiographic changes and/or hypokalemia associated with non–potassium-sparing diuretics may worsen with concomitant beta-agonists. (7.4)
- Anticholinergics: May interact additively with concomitantly used anticholinergic medications. Avoid administration of TRELEGY ELLIPTA with other anticholinergic-containing drugs. (7.5)

8 USE IN SPECIFIC POPULATIONS

Hepatic impairment: Fluticasone furoate systemic exposure may increase in patients with moderate or severe impairment. Monitor for systemic corticosteroid effects. (8.6, 12.3)

FULL PRESCRIBING INFORMATION

1 INDICATIONS AND USAGE

1.1 Maintenance Treatment of Chronic Obstructive Pulmonary Disease

TRELEGY ELLIPTA is indicated for the maintenance treatment of patients with chronic obstructive pulmonary disease (COPD).

1.2 Maintenance Treatment of Asthma

TRELEGY ELLIPTA is indicated for the maintenance treatment of asthma in patients aged 18 years and older.

1.3 Limitations of Use

TRELEGY ELLIPTA is NOT indicated for the relief of acute bronchospasm.

2 DOSAGE AND ADMINISTRATION

2.1 Dosage and Administration Overview

- Administer 1 actuation of TRELEGY ELLIPTA once daily by oral inhalation.
- After inhalation, rinse the mouth with water without swallowing to help reduce the risk of oropharyngeal candidiasis.
- TRELEGY ELLIPTA should be used at the same time every day. Do not use TRELEGY ELLIPTA more than 1 time every 24 hours.
- No dosage adjustment is required for geriatric patients, patients with renal impairment, or patients with moderate hepatic impairment [see Clinical Pharmacology (12.3)].

2.2 Recommended Dosage for Maintenance Treatment of Chronic Obstructive Pulmonary Disease

The recommended dosage of TRELEGY ELLIPTA for maintenance treatment of COPD is fluticasone furoate 100 mcg, umeclidinium 62.5 mcg, and vilanterol 25 mcg (1 actuation of TRELEGY ELLIPTA 100/62.5/25 mcg) once daily by oral inhalation.

- TRELEGY ELLIPTA 100/62.5/25 mcg is the only strength indicated for the treatment of COPD.
- If shortness of breath occurs in the period between doses, an inhaled, short-acting beta2-agonist (rescue medicine, e.g., albuterol) should be used for immediate relief.

2.3 Recommended Dosage for Maintenance Treatment of Asthma

The recommended starting dosage of TRELEGY ELLIPTA for maintenance treatment of asthma is fluticasone furoate 100 mcg, umeclidinium 62.5 mcg, and vilanterol 25 mcg (1 actuation of TRELEGY ELLIPTA 100/62.5/25 mcg) or fluticasone furoate 200 mcg, umeclidinium 62.5 mcg, and vilanterol 25 mcg (1 actuation of TRELEGY ELLIPTA 200/62.5/25 mcg) once daily, by oral inhalation.

- When choosing the starting dosage strength of TRELEGY ELLIPTA, consider the patients’ disease severity; their previous asthma therapy, including the inhaled corticosteroid (ICS) dosage; as well as the patients’ current control of asthma symptoms and risk of future exacerbation.
- The maximum recommended dosage is 1 inhalation of TRELEGY ELLIPTA 200/62.5/25 mcg once daily.
- For patients who do not respond adequately to TRELEGY ELLIPTA 100/62.5/25 mcg once daily, increasing the dose to TRELEGY ELLIPTA 200/62.5/25 mcg once daily may provide additional improvement in asthma control. For patients who do not respond adequately to TRELEGY ELLIPTA 200/62.5/25 mcg once daily, re-evaluate and consider other therapeutic regimens and additional therapeutic options.
- If asthma symptoms arise in the period between doses, an inhaled, short-acting beta2-agonist (rescue medicine, e.g., albuterol) should be used for immediate relief.

3 DOSAGE FORMS AND STRENGTHS

Inhalation powder:

- 100 mcg fluticasone furoate, 62.5 mcg umeclidinium, and 25 mcg vilanterol (100/62.5/25 mcg) per actuation.
- 200 mcg fluticasone furoate, 62.5 mcg umeclidinium, and 25 mcg vilanterol (200/62.5/25 mcg) per actuation.

4 CONTRAINDICATIONS

TRELEGY ELLIPTA is contraindicated in the following conditions:

- Primary treatment of status asthmaticus or other acute episodes of COPD or asthma where intensive measures are required [see Warnings and Precautions (5.2)].
- Severe hypersensitivity to milk proteins or demonstrated hypersensitivity to fluticasone furoate, umeclidinium, vilanterol, or any of the excipients [see Warnings and Precautions (5.11), Description (11)].

5 WARNINGS AND PRECAUTIONS

5.1 Serious Asthma-Related Events – Hospitalizations, Intubations, Death

Use of long-acting beta2-adrenergic agonists (LABA) as monotherapy (without ICS) for asthma is associated with an increased risk of asthma-related death. Available data from controlled clinical trials also suggest that use of LABA as monotherapy increases the risk of asthma-related hospitalization in pediatric and adolescent patients. These findings are considered a class effect of LABA monotherapy. When LABA are used in fixed‑dose combination with ICS, data from large clinical trials do not show a significant increase in the risk of serious asthma-related events (hospitalizations, intubations, death) compared with ICS alone (see Serious Asthma-Related Events with Inhaled Corticosteroid/Long‑acting Beta2-adrenergic Agonists).

Serious Asthma-Related Events with Inhaled Corticosteroid/Long-acting Beta2-adrenergic Agonists

Four (4) large, 26-week, randomized, double-blind, active-controlled clinical safety trials were conducted to evaluate the risk of serious asthma-related events when LABA were used in fixed-dose combination with ICS compared with ICS alone in subjects with asthma. Three (3) trials included adult and adolescent subjects aged 12 years and older: 1 trial compared budesonide/formoterol with budesonide, 1 trial compared fluticasone propionate/salmeterol inhalation powder with fluticasone propionate inhalation powder, and 1 trial compared mometasone furoate/formoterol with mometasone furoate. The fourth trial included pediatric subjects aged 4 to 11 years and compared fluticasone propionate/salmeterol inhalation powder with fluticasone propionate inhalation powder. The primary safety endpoint for all 4 trials was serious asthma-related events (hospitalizations, intubations, death). A blinded adjudication committee determined whether events were asthma related.

The 3 adult and adolescent trials were designed to rule out a risk margin of 2.0, and the pediatric trial was designed to rule out a risk margin of 2.7. Each individual trial met its pre-specified objective and demonstrated non-inferiority of ICS/LABA to ICS alone. A meta-analysis of the 3 adult and adolescent trials did not show a significant increase in risk of a serious asthma-related event with ICS/LABA fixed-dose combination compared with ICS alone (Table 1). These trials were not designed to rule out all risk for serious asthma-related events with ICS/LABA compared with ICS.

Table 1. Meta-analysis of Serious Asthma-Related Events in Subjects with Asthma Aged 12 Years and Older
 | ICS/LABA; (n = 17,537)a | ICS; (n = 17,552)a | ICS/LABA vs. ICS; Hazard Ratio (95% CI)b
Serious asthma-related eventc | 116 | 105 | 1.10 (0.85, 1.44)
Asthma-related death | 2 | 0
Asthma-related intubation (endotracheal) | 1 | 2
Asthma-related hospitalization (≥24-hour stay) | 115 | 105
ICS = Inhaled Corticosteroid, LABA = Long-acting Beta2-adrenergic Agonist.
a Randomized subjects who had taken at least 1 dose of study drug. Planned treatment used for analysis.
b Estimated using a Cox proportional hazards model for time to first event with baseline hazards stratified by each of the 3 trials.
c Number of subjects with event that occurred within 6 months after the first use of study drug or 7 days after the last date of study drug, whichever date was later. Subjects can have 1 or more events, but only the first event was counted for analysis. A single, blinded, independent adjudication committee determined whether events were asthma related.

The pediatric safety trial included 6,208 pediatric subjects aged 4 to 11 years who received ICS/LABA (fluticasone propionate/salmeterol inhalation powder) or ICS (fluticasone propionate inhalation powder). In this trial, 27/3,107 (0.9%) subjects randomized to ICS/LABA and 21/3,101 (0.7%) subjects randomized to ICS experienced a serious asthma-related event. There were no asthma-related deaths or intubations. ICS/LABA did not show a significantly increased risk of a serious asthma-related event compared with ICS based on the pre-specified risk margin (2.7), with an estimated hazard ratio of time to first event of 1.29 (95% CI: 0.73, 2.27). TRELEGY ELLIPTA is not indicated for use in pediatric patients aged 17 years and younger.

Salmeterol Multicenter Asthma Research Trial (SMART)

A 28-week, placebo-controlled, U.S. trial that compared the safety of salmeterol with placebo, each added to usual asthma therapy, showed an increase in asthma-related deaths in subjects receiving salmeterol (13/13,176 in subjects treated with salmeterol vs. 3/13,179 in subjects treated with placebo; relative risk: 4.37 [95% CI: 1.25, 15.34]). Use of background ICS was not required in SMART. The increased risk of asthma-related death is considered a class effect of LABA monotherapy.

5.2 Deterioration of Disease and Acute Episodes

TRELEGY ELLIPTA should not be initiated in patients during rapidly deteriorating or potentially life-threatening episodes of COPD or asthma. TRELEGY ELLIPTA has not been studied in subjects with acutely deteriorating COPD or asthma. The initiation of TRELEGY ELLIPTA in this setting is not appropriate.

If TRELEGY ELLIPTA 100/62.5/25 mcg no longer controls symptoms of bronchoconstriction; the patient’s inhaled, short-acting beta2-agonist becomes less effective; or the patient needs more short-acting beta2-agonist than usual, these may be markers of deterioration of disease. In this setting, re-evaluate the patient and the COPD treatment regimen at once. For COPD, the daily dose of TRELEGY ELLIPTA 100/62.5/25 mcg should not be increased.

Increasing use of inhaled, short-acting beta2-agonists is a marker of deteriorating asthma. In this situation, the patient requires immediate reevaluation with reassessment of the treatment regimen, giving special consideration to the need for additional therapeutic options. Patients should not use more than 1 inhalation once daily of TRELEGY ELLIPTA.

TRELEGY ELLIPTA should not be used for the relief of acute symptoms, i.e., as rescue therapy for the treatment of acute episodes of bronchospasm. TRELEGY ELLIPTA has not been studied in the relief of acute symptoms and extra doses should not be used for that purpose. Acute symptoms should be treated with an inhaled, short-acting beta2-agonist.

When beginning treatment with TRELEGY ELLIPTA, patients who have been taking oral or inhaled, short-acting beta2-agonists on a regular basis (e.g., 4 times a day) should be instructed to discontinue the regular use of these drugs and to use them only for symptomatic relief of acute respiratory symptoms. When prescribing TRELEGY ELLIPTA, the healthcare provider should also prescribe an inhaled, short-acting beta2-agonist and instruct the patient on how it should be used.

5.3 Avoid Excessive Use of TRELEGY ELLIPTA and Avoid Use with Other Long-acting Beta2-agonists

TRELEGY ELLIPTA should not be used more often than recommended, at higher doses than recommended, or in conjunction with other therapies containing LABA, as an overdose may result. Clinically significant cardiovascular effects and fatalities have been reported in association with excessive use of inhaled sympathomimetic drugs. Patients using TRELEGY ELLIPTA should not use another therapy containing a LABA (e.g., salmeterol, formoterol fumarate, arformoterol tartrate, indacaterol) for any reason.

5.4 Oropharyngeal Candidiasis

TRELEGY ELLIPTA contains fluticasone furoate, an ICS. Localized infections of the mouth and pharynx with Candida albicans have occurred in subjects treated with orally inhaled drug products containing fluticasone furoate. When such an infection develops, it should be treated with appropriate local or systemic (i.e., oral) antifungal therapy while treatment with TRELEGY ELLIPTA continues. In some cases, therapy with TRELEGY ELLIPTA may need to be interrupted. Advise the patient to rinse his/her mouth with water without swallowing following administration of TRELEGY ELLIPTA to help reduce the risk of oropharyngeal candidiasis.

5.5 Pneumonia

Lower respiratory tract infections, including pneumonia, have been reported following the inhaled administration of corticosteroids.

Physicians should remain vigilant for the possible development of pneumonia in patients with COPD as clinical features of pneumonia and exacerbations frequently overlap.

In two 12-week trials of subjects with COPD (N = 824), the incidence of pneumonia was <1% for both treatment arms: umeclidinium 62.5 mcg + fluticasone furoate/vilanterol 100/25 mcg or placebo + fluticasone furoate/vilanterol 100/25 mcg. Fatal pneumonia occurred in 1 subject receiving placebo + fluticasone furoate/vilanterol 100/25 mcg.

In a 52-week trial of subjects with COPD (N = 10,355), the incidence of pneumonia was 8% for TRELEGY ELLIPTA 100/62.5/25 mcg (n = 4,151), 7% for fluticasone furoate/vilanterol 100/25 mcg (n = 4,134), and 5% for umeclidinium/vilanterol 62.5/25 mcg (n = 2,070). Fatal pneumonia occurred in 12 of 4,151 patients (0.35 per 100 patient-years) receiving TRELEGY ELLIPTA 100/62.5/25 mcg; 5 of 4,134 patients (0.17 per 100 patient-years) receiving fluticasone furoate/vilanterol 100/25 mcg; and 5 of 2,070 patients (0.29 per 100 patient-years) receiving umeclidinium/vilanterol 62.5/25 mcg.

In a mortality trial with fluticasone furoate/vilanterol 100/25 mcg with a median treatment duration of 1.5 years in 16,568 subjects with moderate COPD and cardiovascular disease, the annualized incidence rate of pneumonia was 3.4 per 100 patient-years for fluticasone furoate/vilanterol 100/25 mcg, 3.2 for placebo, 3.3 for fluticasone furoate 100 mcg, and 2.3 for vilanterol 25 mcg. Adjudicated, on‑treatment deaths due to pneumonia occurred in 13 subjects receiving fluticasone furoate/vilanterol 100/25 mcg, 9 subjects receiving placebo, 10 subjects receiving fluticasone furoate 100 mcg, and 6 subjects receiving vilanterol 25 mcg (<0.2 per 100 patient-years for each treatment group).

5.6 Immunosuppression and Risk of Infections

Persons who are using drugs that suppress the immune system are more susceptible to infections than healthy individuals. Chickenpox and measles can have a more serious or even fatal course in susceptible children or adults using corticosteroids. In such children or adults who have not had these diseases or been properly immunized, particular care should be taken to avoid exposure. How the dose, route, and duration of corticosteroid administration affect the risk of developing a disseminated infection is not known. The safety and effectiveness of TRELEGY have not been established in pediatric patients and TRELEGY is not indicated for use in this population. The contribution of the underlying disease and/or prior corticosteroid treatment to the risk is also not known. If a patient is exposed to chickenpox, prophylaxis with varicella zoster immune globulin (VZIG) may be indicated. If a patient is exposed to measles, prophylaxis with pooled intramuscular immunoglobulin (IG) may be indicated. (See the respective Prescribing Information for VZIG and IG.) If chickenpox develops, treatment with antiviral agents may be considered.

ICS should be used with caution, if at all, in patients with active or quiescent tuberculosis infections of the respiratory tract; systemic fungal, bacterial, viral, or parasitic infections; or ocular herpes simplex.

5.7 Transferring Patients from Systemic Corticosteroid Therapy

HPA Suppression/Adrenal Insufficiency

Particular care is needed for patients who have been transferred from systemically active corticosteroids to ICS because deaths due to adrenal insufficiency have occurred in patients during and after transfer from systemic corticosteroids to less systemically available ICS. After withdrawal from systemic corticosteroids, a number of months are required for recovery of hypothalamic-pituitary-adrenal (HPA) function.

Patients who have been previously maintained on 20 mg or more of prednisone (or its equivalent) may be most susceptible, particularly when their systemic corticosteroids have been almost completely withdrawn. During this period of HPA suppression, patients may exhibit signs and symptoms of adrenal insufficiency when exposed to trauma, surgery, or infection (particularly gastroenteritis) or other conditions associated with severe electrolyte loss. Although TRELEGY ELLIPTA may control COPD or asthma symptoms during these episodes, in recommended doses it supplies less than normal physiological amounts of glucocorticoid systemically and does NOT provide the mineralocorticoid activity that is necessary for coping with these emergencies.

During periods of stress, a severe COPD exacerbation, or a severe asthma attack, patients who have been withdrawn from systemic corticosteroids should be instructed to resume oral corticosteroids (in large doses) immediately and to contact their health care practitioner for further instruction. These patients should also be instructed to carry a warning card indicating that they may need supplementary systemic corticosteroids during periods of stress, a severe COPD exacerbation, or a severe asthma attack.

Patients requiring oral corticosteroids should be weaned slowly from systemic corticosteroid use after transferring to TRELEGY ELLIPTA. Prednisone reduction can be accomplished by reducing the daily prednisone dose by 2.5 mg on a weekly basis during therapy with TRELEGY ELLIPTA. Lung function (FEV1), beta-agonist use, and COPD or asthma symptoms should be carefully monitored during withdrawal of oral corticosteroids. In addition, patients should be observed for signs and symptoms of adrenal insufficiency, such as fatigue, lassitude, weakness, nausea and vomiting, and hypotension.

Unmasking of Allergic Conditions Previously Suppressed by Systemic Corticosteroids

Transfer of patients from systemic corticosteroid therapy to TRELEGY ELLIPTA may unmask allergic conditions previously suppressed by the systemic corticosteroid therapy (e.g., rhinitis, conjunctivitis, eczema, arthritis, eosinophilic conditions).

Corticosteroid Withdrawal Symptoms

During withdrawal from oral corticosteroids, some patients may experience symptoms of systemically active corticosteroid withdrawal (e.g., joint and/or muscular pain, lassitude, depression) despite maintenance or even improvement of respiratory function.

5.8 Hypercorticism and Adrenal Suppression

Inhaled fluticasone furoate is absorbed into the circulation and can be systemically active. Effects of fluticasone furoate on the HPA axis are not observed with the therapeutic doses of fluticasone furoate in TRELEGY ELLIPTA. However, exceeding the recommended dosage or coadministration with a strong cytochrome P450 3A4 (CYP3A4) inhibitor may result in HPA dysfunction [see Warnings and Precautions (5.9), Drug Interactions (7.1)].

Because of the possibility of significant systemic absorption of ICS in sensitive patients, patients treated with TRELEGY ELLIPTA should be observed carefully for any evidence of systemic corticosteroid effects. Particular care should be taken in observing patients postoperatively or during periods of stress for evidence of inadequate adrenal response.

It is possible that systemic corticosteroid effects such as hypercorticism and adrenal suppression (including adrenal crisis) may appear in a small number of patients who are sensitive to these effects. If such effects occur, reduce the dose of TRELEGY ELLIPTA slowly, consistent with accepted procedures for reducing systemic corticosteroids, and consider other treatments for management of COPD or asthma symptoms.

5.9 Drug Interactions with Strong Cytochrome P450 3A4 Inhibitors

Caution should be exercised when considering the coadministration of TRELEGY ELLIPTA with ketoconazole and other known strong CYP3A4 inhibitors (including, but not limited to, ritonavir, clarithromycin, conivaptan, indinavir, itraconazole, lopinavir, nefazodone, nelfinavir, saquinavir, telithromycin, troleandomycin, voriconazole) because increased systemic corticosteroid and increased cardiovascular adverse effects may occur [see Drug Interactions (7.1), Clinical Pharmacology (12.3)].

5.10 Paradoxical Bronchospasm

As with other inhaled therapies, TRELEGY ELLIPTA can produce paradoxical bronchospasm, which may be life threatening. If paradoxical bronchospasm occurs following dosing with TRELEGY ELLIPTA, it should be treated immediately with an inhaled, short-acting bronchodilator; TRELEGY ELLIPTA should be discontinued immediately; and alternative therapy should be instituted.

5.11 Hypersensitivity Reactions, including Anaphylaxis

Hypersensitivity reactions such as anaphylaxis, angioedema, rash, and urticaria may occur after administration of TRELEGY ELLIPTA. Discontinue TRELEGY ELLIPTA if such reactions occur. There have been reports of anaphylactic reactions in patients with severe milk protein allergy after inhalation of other powder medications containing lactose; therefore, patients with severe milk protein allergy should not use TRELEGY ELLIPTA [see Contraindications (4), Adverse Reactions (6.3)].

5.12 Cardiovascular Effects

Vilanterol, like other beta2-agonists, can produce a clinically significant cardiovascular effect in some patients as measured by increases in pulse rate, systolic or diastolic blood pressure, and also cardiac arrhythmias, such as supraventricular tachycardia and extrasystoles. If such effects occur, TRELEGY ELLIPTA may need to be discontinued. In addition, beta-agonists have been reported to produce electrocardiographic changes, such as flattening of the T wave, prolongation of the QTc interval, and ST segment depression, although the clinical significance of these findings is unknown [see Clinical Pharmacology (12.2)]. Fatalities have been reported in association with excessive use of inhaled sympathomimetic drugs.

TRELEGY ELLIPTA, like other sympathomimetic amines, should be used with caution in patients with cardiovascular disorders, especially coronary insufficiency, cardiac arrhythmias, and hypertension.

In a 52-week trial of subjects with COPD, the exposure-adjusted rates for any on-treatment major adverse cardiac event, including non-fatal central nervous system hemorrhages and cerebrovascular conditions, non-fatal myocardial infarction (MI), non-fatal acute MI, and adjudicated on-treatment death due to cardiovascular events, was 2.2 per 100 patient-years for TRELEGY ELLIPTA (n = 4,151), 1.9 per 100 patient-years for fluticasone furoate/vilanterol 100/25 mcg (n = 4,134), and 2.2 per 100 patient-years for umeclidinium/vilanterol 62.5/25 mcg (n = 2,070). Adjudicated on-treatment deaths due to cardiovascular events occurred in 20 of 4,151 patients (0.54 per 100 patient-years) receiving TRELEGY ELLIPTA; 27 of 4,134 patients (0.78 per 100 patient-years) receiving fluticasone furoate/vilanterol; and 16 of 2,070 patients (0.94 per 100 patient-years) receiving umeclidinium/vilanterol.

In a mortality trial with fluticasone furoate/vilanterol with a median treatment duration of 1.5 years in 16,568 subjects with moderate COPD and cardiovascular disease, the annualized incidence rate of adjudicated cardiovascular events (composite of myocardial infarction, stroke, unstable angina, transient ischemic attack, or on-treatment death due to cardiovascular events) was 2.5 per 100 patient-years for fluticasone furoate/vilanterol 100/25 mcg, 2.7 for placebo, 2.4 for fluticasone furoate 100 mcg, and 2.6 for vilanterol 25 mcg. Adjudicated, on-treatment deaths due to cardiovascular events occurred in 82 subjects receiving fluticasone furoate/vilanterol 100/25 mcg, 86 subjects receiving placebo, 80 subjects receiving fluticasone furoate 100 mcg, and 90 subjects receiving vilanterol 25 mcg (annualized incidence rate ranged from 1.2 to 1.3 per 100 patient-years for the treatment groups).

5.13 Reduction in Bone Mineral Density

Decreases in bone mineral density (BMD) have been observed with long-term administration of products containing ICS. The clinical significance of small changes in BMD with regard to long‑term consequences such as fracture is unknown. Patients with major risk factors for decreased bone mineral content, such as prolonged immobilization, family history of osteoporosis, postmenopausal status, tobacco use, advanced age, poor nutrition, or chronic use of drugs that can reduce bone mass (e.g., anticonvulsants, oral corticosteroids) should be monitored and treated with established standards of care. Since patients with COPD often have multiple risk factors for reduced BMD, assessment of BMD is recommended prior to initiating TRELEGY ELLIPTA and periodically thereafter. If significant reductions in BMD are seen and TRELEGY ELLIPTA is still considered medically important for that patient’s COPD therapy, use of therapy to treat or prevent osteoporosis should be strongly considered.

5.14 Glaucoma and Cataracts, Worsening of Narrow-Angle Glaucoma

Glaucoma, increased intraocular pressure, and cataracts have been reported in patients with COPD or asthma following the long-term administration of ICS or with use of inhaled anticholinergics. TRELEGY ELLIPTA should be used with caution in patients with narrow-angle glaucoma. Prescribers and patients should also be alert for signs and symptoms of acute narrow‑angle glaucoma (e.g., eye pain or discomfort, blurred vision, visual halos or colored images in association with red eyes from conjunctival congestion and corneal edema). Instruct patients to consult a healthcare provider immediately if any of these signs or symptoms develop. Consider referral to an ophthalmologist in patients who develop ocular symptoms or use TRELEGY ELLIPTA long term.

5.15 Worsening of Urinary Retention

TRELEGY ELLIPTA, like all therapies containing an anticholinergic, should be used with caution in patients with urinary retention. Prescribers and patients should be alert for signs and symptoms of urinary retention (e.g., difficulty passing urine, painful urination), especially in patients with prostatic hyperplasia or bladder-neck obstruction. Instruct patients to consult a healthcare provider immediately if any of these signs or symptoms develop.

5.16 Coexisting Conditions

TRELEGY ELLIPTA, like all therapies containing sympathomimetic amines, should be used with caution in patients with convulsive disorders or thyrotoxicosis and in those who are unusually responsive to sympathomimetic amines. Doses of the related beta2-adrenoceptor agonist albuterol, when administered intravenously, have been reported to aggravate preexisting diabetes mellitus and ketoacidosis.

5.17 Hypokalemia and Hyperglycemia

Beta-adrenergic agonist therapies may produce significant hypokalemia in some patients, possibly through intracellular shunting, which has the potential to produce adverse cardiovascular effects. The decrease in serum potassium is usually transient, not requiring supplementation. Beta-agonist therapies may produce transient hyperglycemia in some patients.

5.18 Effect on Growth

Orally inhaled corticosteroids may cause a reduction in growth velocity when administered to children and adolescents. The safety and effectiveness of TRELEGY have not been established in pediatric patients (aged 17 years and younger) and TRELEGY is not indicated for use in this population. [See Use in Specific Populations (8.4).]

6 ADVERSE REACTIONS

The following clinically significant adverse reactions are described elsewhere in labeling:

- Serious Asthma-Related Events – Hospitalizations, Intubations, Death [see Warnings and Precautions (5.1)]
- Oropharyngeal Candidiasis [see Warnings and Precautions (5.4)]
- Increased Risk of Pneumonia in COPD [see Warnings and Precautions (5.5)]
- Immunosuppression and Risk of Infections [see Warnings and Precautions (5.6)]
- Hypercorticism and Adrenal Suppression [see Warnings and Precautions (5.8)]
- Paradoxical Bronchospasm [see Warnings and Precautions (5.10)]
- Cardiovascular Effects [see Warnings and Precautions (5.12)]
- Reduction in Bone Mineral Density [see Warnings and Precautions (5.13)]
- Worsening of Narrow-Angle Glaucoma [see Warnings and Precautions (5.14)]
- Worsening of Urinary Retention [see Warnings and Precautions (5.15)]

Because clinical trials are conducted under widely varying conditions, adverse reaction rates observed in the clinical trials of a drug cannot be directly compared with rates in the clinical trials of another drug and may not reflect the rates observed in practice.

6.1 Clinical Trials Experience in Chronic Obstructive Pulmonary Disease

The safety of TRELEGY ELLIPTA in COPD is based on the safety data from two 12-week treatment trials with coadministration of umeclidinium and the fixed-dose combination of fluticasone furoate/vilanterol and a 52-week long-term trial of TRELEGY ELLIPTA 100/62.5/25 mcg compared with the fixed-dose combinations of fluticasone furoate/vilanterol and umeclidinium/vilanterol [see Clinical Studies (14.1)].

Trials 1 and 2

Two 12-week treatment trials (Trial 1 and Trial 2) evaluated the coadministration of umeclidinium + fluticasone furoate/vilanterol, the components of TRELEGY ELLIPTA, compared with placebo + fluticasone furoate/vilanterol. A total of 824 subjects with COPD across two 12-week, randomized, double-blind clinical trials received at least 1 dose of umeclidinium 62.5 mcg + fluticasone furoate/vilanterol 100/25 mcg or placebo + fluticasone furoate/vilanterol 100/25 mcg administered once daily (mean age: 64 years, 92% White, 66% male across all treatments) [see Clinical Studies (14.1)]. The incidence of adverse reactions associated with the use of umeclidinium 62.5 mcg + fluticasone furoate/vilanterol 100/25 mcg presented in Table 2 is based on the two 12-week trials.

Table 2. Adverse Reactions with Umeclidinium + Fluticasone Furoate/Vilanterol with ≥1% Incidence and More Common than Placebo + Fluticasone Furoate/Vilanterol in Subjects with COPD (Trials 1 and 2)
Adverse Reaction | Umec + FF/VI; (n = 412); % | Placebo + FF/VI; (n = 412); %
Nervous system disorders
Headache | 4 | 3
Dysgeusia | 2 | <1
Musculoskeletal and connective tissue disorders
Back pain | 4 | 2
Respiratory, thoracic, and mediastinal disorders
Cough | 1 | <1
Oropharyngeal pain | 1 | 0
Gastrointestinal disorders
Diarrhea | 2 | <1
Infections and infestations
Gastroenteritis | 1 | 0
Umec = Umeclidinium, FF/VI = Fluticasone Furoate/Vilanterol.

Trial 3 – Long-term Safety Data

A 52-week trial (Trial 3) evaluated the long-term safety of TRELEGY ELLIPTA 100/62.5/25 mcg compared with the fixed-dose combinations of fluticasone furoate/vilanterol 100/25 mcg and umeclidinium/vilanterol 62.5/25 mcg. A total of 10,355 subjects with COPD with a history of moderate or severe exacerbations within the prior 12 months were randomized (2:2:1) to receive TRELEGY ELLIPTA 100/62.5/25 mcg, fluticasone furoate/vilanterol, or umeclidinium/vilanterol administered once daily in a double‑blind clinical trial (mean age: 65 years, 77% White, 66% male across all treatments) [see Clinical Studies (14.1)].

The incidence of adverse reactions in the long-term trial were consistent with those in Trials 1 and 2. However, in addition to the adverse reactions shown in Table 2, adverse reactions occurring in ≥1% of the subjects treated with TRELEGY ELLIPTA 100/62.5/25 mcg (n = 4,151) for up to 52 weeks also included upper respiratory tract infection, pneumonia [see Warnings and Precautions (5.5)], bronchitis, oral candidiasis [see Warnings and Precautions (5.4)], arthralgia, influenza, sinusitis, pharyngitis, rhinitis, constipation, urinary tract infection, and dysphonia.

6.2 Clinical Trials Experience in Asthma

The safety of TRELEGY ELLIPTA in asthma is based on a randomized, double-blind, parallel‑group, active-controlled trial of 24 to 52 weeks’ duration (Trial 4) that enrolled 2,436 adult subjects inadequately controlled on their current treatment of combination therapy (ICS plus a LABA) [see Clinical Studies (14.2)]. In the overall population, 62% were female and 80% were White; mean age was 53 years. The incidence of adverse reactions occurring in ≥1% of the subjects treated with TRELEGY ELLIPTA 100/62.5/25 mcg or TRELEGY ELLIPTA 200/62.5/25 mcg is shown in Table 3. Adverse reactions observed for the groups treated with TRELEGY ELLIPTA were similar to those observed for the fluticasone furoate/vilanterol arms.

Table 3. Adverse Reactions with TRELEGY ELLIPTA with ≥1% Incidence in Subjects with Asthma (Trial 4)
Adverse Reaction | TRELEGY ELLIPTA; 200/62.5/25 mcg; (n = 408); % | TRELEGY ELLIPTA; 100/62.5/25 mcg; (n =406); % | FF/VI; 200/25 mcg; (n = 406); % | FF/VI; 100/25 mcg; (n = 407); %
Infections and infestations
Pharyngitis/nasopharyngitis | 15 | 17 | 16 | 16
Upper respiratory tract infection/viral upper respiratory tract infection | 7 | 5 | 6 | 7
Bronchitis | 5 | 4 | 5 | 3
Respiratory tract infection/viral respiratory tract infection | 3 | 4 | 2 | 4
Sinusitis/acute sinusitis | 3 | 2 | 2 | 3
Urinary tract infection | 2 | <1 | <1 | 1
Rhinitis | 1 | 2 | 2 | 3
Influenza | 1 | 4 | 2 | 3
Pneumonia | <1 | 1 | 2 | 2
Nervous system disorders
Headache | 5 | 9 | 6 | 7
Musculoskeletal and connective tissue disorders
Back pain | 2 | 3 | 1 | 4
Respiratory, thoracic, and mediastinal disorders
Dysphonia | 1 | 1 | 2 | 1
Oropharyngeal pain | 1 | 1 | <1 | <1
Cough | 1 | <1 | 1 | 1
FF/VI = Fluticasone Furoate/Vilanterol.

6.3 Postmarketing Experience

In addition to adverse reactions reported from clinical trials, the following adverse reactions have been identified during postapproval use of TRELEGY ELLIPTA. Because these reactions are reported voluntarily from a population of uncertain size, it is not always possible to reliably estimate their frequency or establish a causal relationship to drug exposure. These events have been chosen for inclusion due to either their seriousness, frequency of reporting, or causal connection to TRELEGY ELLIPTA or a combination of these factors.

Cardiac Disorders

Palpitations

Eye Disorders

Blurred vision, eye pain, glaucoma, and intraocular pressure increase

Immune System Disorders

Hypersensitivity reactions, including anaphylaxis, angioedema, rash, and urticaria

Metabolism and Nutrition Disorders

Hyperglycemia

Musculoskeletal and Connective Tissue Disorders

Muscle spasms

Nervous System Disorders

Tremor

Psychiatric Disorders

Anxiety

Renal and Urinary Disorders

Dysuria, urinary retention.

7 DRUG INTERACTIONS

7.1 Inhibitors of Cytochrome P450 3A4

Fluticasone furoate and vilanterol are substrates of CYP3A4. Concomitant administration of the strong CYP3A4 inhibitor ketoconazole increases the systemic exposure to fluticasone furoate and vilanterol. Caution should be exercised when considering the coadministration of TRELEGY ELLIPTA with ketoconazole and other known strong CYP3A4 inhibitors [see Warnings and Precautions (5.9), Clinical Pharmacology (12.3)].

7.2 Monoamine Oxidase Inhibitors, Tricyclic Antidepressants, and QTc Prolonging Drugs

Vilanterol, like other beta2-agonists, should be administered with extreme caution to patients being treated with monoamine oxidase inhibitors, tricyclic antidepressants, or drugs known to prolong the QTc interval or within 2 weeks of discontinuation of such agents, because the effect of adrenergic agonists on the cardiovascular system may be potentiated by these agents. Drugs that are known to prolong the QTc interval have an increased risk of ventricular arrhythmias.

7.3 Beta-adrenergic Receptor Blocking Agents

Beta-blockers not only block the pulmonary effect of beta-agonists, such as vilanterol, but may also produce severe bronchospasm in patients with COPD or asthma. Therefore, patients with COPD or asthma should not normally be treated with beta-blockers. However, under certain circumstances, there may be no acceptable alternatives to the use of beta-adrenergic blocking agents for these patients; cardioselective beta-blockers could be considered, although they should be administered with caution.

7.4 Non–Potassium-Sparing Diuretics

The electrocardiographic changes and/or hypokalemia that may result from the administration of non–potassium-sparing diuretics (such as loop or thiazide diuretics) can be acutely worsened by beta-agonists, especially when the recommended dose of the beta-agonist is exceeded. Although the clinical significance of these effects is not known, caution is advised in the coadministration of beta-agonists with non–potassium-sparing diuretics.

7.5 Anticholinergics

There is potential for an additive interaction with concomitantly used anticholinergic medicines. Therefore, avoid coadministration of TRELEGY ELLIPTA with other anticholinergic-containing drugs as this may lead to an increase in anticholinergic adverse effects [see Warnings and Precautions (5.14, 5.15)].

8 USE IN SPECIFIC POPULATIONS

8.1 Pregnancy

Risk Summary

There are insufficient data on the use of TRELEGY ELLIPTA or its individual components, fluticasone furoate, umeclidinium, and vilanterol, in pregnant women to inform a drug‑associated risk. (See Clinical Considerations.) In an animal reproduction study, fluticasone furoate and vilanterol administered by inhalation alone or in combination to pregnant rats during the period of organogenesis produced no fetal structural abnormalities. The highest fluticasone furoate and vilanterol doses in this study were approximately 4.5 and 40 times the maximum recommended human daily inhalation doses (MRHDID) of 200 and 25 mcg, respectively in adults. (See Data.) Umeclidinium administered via inhalation or subcutaneously to pregnant rats and rabbits was not associated with adverse effect on embryofetal development at exposures approximately 40 and 150 times, respectively, the human exposure at the MRHDID of 62.5 mcg. (See Data.)

The estimated risk of major birth defects and miscarriage for the indicated populations is unknown. In the U.S. general population, the estimated risk of major birth defects and miscarriage in clinically recognized pregnancies is 2% to 4% and 15% to 20%, respectively.

Clinical Considerations

Disease-Associated Maternal and/or Embryofetal Risk: In women with poorly or moderately controlled asthma, there is an increased risk of several perinatal outcomes such as pre-eclampsia in the mother and prematurity, low birth weight, and small for gestational age in the neonate. Pregnant women should be closely monitored and medication adjusted as necessary to maintain optimal control of asthma.

Labor or Delivery: TRELEGY ELLIPTA should be used during late gestation and labor only if the potential benefit justifies the potential for risks related to beta-agonists interfering with uterine contractility.

Data

Animal Data: The combination of fluticasone furoate, umeclidinium, and vilanterol has not been studied in pregnant animals. Studies in pregnant animals have been conducted with fluticasone furoate and vilanterol in combination and individually with fluticasone furoate, umeclidinium, or vilanterol.

Fluticasone Furoate and Vilanterol: In an embryofetal developmental study, pregnant rats received fluticasone furoate and vilanterol during the period of organogenesis at doses up to approximately 4.5 and 40 times the MRHDID of 200 and 25 mcg, respectively, alone or in combination (on a mcg/m^2 basis at inhalation doses up to approximately 95 mcg/kg/day). No evidence of structural abnormalities was observed.

Fluticasone Furoate: In 2 separate embryofetal developmental studies, pregnant rats and rabbits received fluticasone furoate during the period of organogenesis at doses up to approximately 4.5 times and equal to, respectively, the MRHDID of 200 mcg (on a mcg/m^2 basis at maternal inhalation doses up to 91 and 8 mcg/kg/day, respectively). No evidence of structural abnormalities in fetuses was observed in either species. In a perinatal and postnatal developmental study in rats, dams received fluticasone furoate during late gestation and lactation periods at doses up to approximately 1.5 times the MRHDID of 200 mcg (on a mcg/m^2 basis at maternal inhalation doses up to 27 mcg/kg/day). No evidence of effects on offspring development was observed.

Umeclidinium: In 2 separate embryofetal developmental studies, pregnant rats and rabbits received umeclidinium during the period of organogenesis at doses up to approximately 40 and 150 times, respectively the MRHDID of 62.5 mcg (on an AUC basis at maternal inhalation doses up to 278 mcg/kg/day in rats and at maternal subcutaneous doses up to 180 mcg/kg/day in rabbits). No evidence of teratogenic effects was observed in either species. In a perinatal and postnatal developmental study in rats, dams received umeclidinium during late gestation and lactation periods at doses up to approximately 20 times the MRHDID (on an AUC basis at maternal subcutaneous doses up to 60 mcg/kg/day). No evidence of effects on offspring development was observed.

Vilanterol: In 2 separate embryofetal developmental studies, pregnant rats and rabbits received vilanterol during the period of organogenesis at doses up to approximately 13,000 and 760 times, respectively, the MRHDID (on a mcg/m^2 basis at maternal inhalation doses up to 33,700 mcg/kg/day in rats and on an AUC basis at maternal inhaled doses up to 5,740 mcg/kg/day in rabbits). No evidence of structural abnormalities was observed at any dose in rats or in rabbits up to approximately 120 times the MRHDID (on an AUC basis at maternal doses up to 591 mcg/kg/day). However, fetal skeletal variations were observed in rabbits at approximately 760 or 840 times the MRHDID (on an AUC basis at maternal inhaled or subcutaneous doses of 5,740 or 300 mcg/kg/day, respectively). The skeletal variations included decreased or absent ossification in cervical vertebral centrum and metacarpals. In a perinatal and postnatal developmental study in rats, dams received vilanterol during late gestation and the lactation periods at doses up to approximately 3,900 times the MRHDID (on a mcg/m^2 basis at maternal oral doses up to 10,000 mcg/kg/day). No evidence of effects in offspring development was observed.

8.2 Lactation

Risk Summary

There is no information available on the presence of fluticasone furoate, umeclidinium, or vilanterol in human milk; the effects on the breastfed child; or the effects on milk production. Umeclidinium was detected in the plasma of offspring of lactating rats treated with umeclidinium, suggesting its presence in maternal milk. (See Data.) The developmental and health benefits of breastfeeding should be considered along with the mother’s clinical need for TRELEGY ELLIPTA and any potential adverse effects on the breastfed child from fluticasone furoate, umeclidinium, or vilanterol or from the underlying maternal condition.

Data

Subcutaneous administration of umeclidinium to lactating rats at greater than or equal to 60 mcg/kg/day resulted in a quantifiable level of umeclidinium in 2 of 54 pups, which may indicate transfer of umeclidinium in rat milk.

8.4 Pediatric Use

The safety and effectiveness of TRELEGY ELLIPTA have not been established in pediatric patients (aged 17 years and younger). TRELEGY ELLIPTA is not indicated for use in pediatric patients.

Effects on Growth

Orally inhaled corticosteroids may cause a reduction in growth velocity when administered to children and adolescents.

Controlled clinical trials have shown that ICS may cause a reduction in growth in children. In these trials, the mean reduction in growth velocity was approximately 1 cm/year (range: 0.3 to 1.8 cm/year) and appears to be related to dose and duration of exposure. This effect has been observed in the absence of laboratory evidence of HPA axis suppression, suggesting that growth velocity is a more sensitive indicator of systemic corticosteroid exposure in children than some commonly used tests of HPA axis function. The long-term effects of this reduction in growth velocity associated with orally inhaled corticosteroids, including the impact on final adult height, are unknown.

A randomized, double-blind, parallel-group, multicenter, 1-year, placebo-controlled trial evaluated the effect of once-daily treatment with 110 mcg of fluticasone furoate in the nasal spray formulation on growth velocity assessed by stadiometry. The subjects were 474 prepubescent children (girls aged 5 to 7.5 years and boys aged 5 to 8.5 years). Mean growth velocity over the 52-week treatment period was lower in the subjects receiving fluticasone furoate nasal spray (5.19 cm/year) compared with placebo (5.46 cm/year). The mean reduction in growth velocity was 0.27 cm/year (95% CI: 0.06, 0.48) [see Warnings and Precautions (5.18)].

8.5 Geriatric Use

Based on available data, no adjustment of the dosage of TRELEGY ELLIPTA in geriatric patients is necessary, but greater sensitivity in some older individuals cannot be ruled out.

In COPD Trials 1 and 2 (coadministration trials), 189 subjects aged 65 years and older, of which 39 subjects were aged 75 years and older, were administered umeclidinium 62.5 mcg + fluticasone furoate/vilanterol 100/25 mcg. In COPD Trial 3, 2,265 subjects aged 65 years and older, of which 565 subjects were aged 75 years and older, were administered TRELEGY ELLIPTA. In an asthma clinical trial (Trial 4), 159 subjects aged 65 years and older, of which 27 subjects were aged 75 years and older, were administered TRELEGY ELLIPTA 100/62.5/25 mcg or TRELEGY ELLIPTA 200/62.5/25 mcg. No overall differences in safety or effectiveness were observed between these subjects and younger subjects, and other reported clinical experience has not identified differences in responses between the elderly and younger subjects.

8.6 Hepatic Impairment

TRELEGY ELLIPTA has not been studied in subjects with hepatic impairment. Information on the individual components is provided below.

Fluticasone Furoate/Vilanterol

Fluticasone furoate systemic exposure increased by up to 3-fold in subjects with hepatic impairment compared with healthy subjects. Hepatic impairment had no effect on vilanterol systemic exposure. Use TRELEGY ELLIPTA with caution in patients with moderate or severe hepatic impairment. Monitor patients for corticosteroid-related side effects [see Clinical Pharmacology (12.3)].

Umeclidinium

Patients with moderate hepatic impairment (Child-Pugh score of 7-9) showed no relevant increases in Cmax or AUC, nor did protein binding differ between subjects with moderate hepatic impairment and their healthy controls. Studies in subjects with severe hepatic impairment have not been performed [see Clinical Pharmacology (12.3)].

8.7 Renal Impairment

TRELEGY ELLIPTA has not been studied in subjects with renal impairment. Information on the individual components is provided below.

Fluticasone Furoate/Vilanterol

There were no significant increases in either fluticasone furoate or vilanterol exposure in subjects with severe renal impairment (CrCl <30 mL/min) compared with healthy subjects. No dosage adjustment is required in patients with renal impairment [see Clinical Pharmacology (12.3)].

Umeclidinium

Patients with severe renal impairment (CrCl <30 mL/min) showed no relevant increases in Cmax or AUC, nor did protein binding differ between subjects with severe renal impairment and their healthy controls. No dosage adjustment is required in patients with renal impairment [see Clinical Pharmacology (12.3)].

10 OVERDOSAGE

TRELEGY ELLIPTA contains fluticasone furoate, umeclidinium, and vilanterol; therefore, the risks associated with overdosage for the individual components described below apply to TRELEGY ELLIPTA. Treatment of overdosage consists of discontinuation of TRELEGY ELLIPTA together with institution of appropriate symptomatic and/or supportive therapy. The judicious use of a cardioselective beta-receptor blocker may be considered, bearing in mind that such medicine can produce bronchospasm. Cardiac monitoring is recommended in cases of overdosage.

Fluticasone Furoate

Because of low systemic bioavailability (15.2%) and an absence of acute drug-related systemic findings in clinical trials, overdosage of fluticasone furoate is unlikely to require any treatment other than observation. If used at excessive doses for prolonged periods, systemic effects such as hypercorticism may occur [see Warnings and Precautions (5.8)].

Umeclidinium

High doses of umeclidinium may lead to anticholinergic signs and symptoms.

Vilanterol

The expected signs and symptoms with overdosage of vilanterol are those of excessive beta‑adrenergic stimulation and/or occurrence or exaggeration of any of the signs and symptoms of beta-adrenergic stimulation (e.g., seizures, angina, hypertension or hypotension, tachycardia with rates up to 200 beats/min, arrhythmias, nervousness, headache, tremor, muscle cramps, dry mouth, palpitation, nausea, dizziness, fatigue, malaise, insomnia, hyperglycemia, hypokalemia, metabolic acidosis). As with all inhaled sympathomimetic medicines, cardiac arrest and even death may be associated with an overdose of vilanterol.

11 DESCRIPTION

TRELEGY ELLIPTA is an inhalation powder drug product for delivery of a combination of fluticasone furoate (an ICS), umeclidinium (an anticholinergic), and vilanterol (a LABA) to patients by oral inhalation.

Fluticasone furoate, a synthetic trifluorinated corticosteroid, has the chemical name (6α,11β,16α,17α)-6,9-difluoro-17-{[(fluoro-methyl)thio]carbonyl}-11-hydroxy-16-methyl-3-oxoandrosta-1,4-dien-17-yl 2-furancarboxylate and the following chemical structure:

Fluticasone furoate is a white powder with a molecular weight of 538.6, and the empirical formula is C27H29F3O6S. It is practically insoluble in water.

Umeclidinium bromide has the chemical name 1-[2-(benzyloxy)ethyl]-4-(hydroxydiphenylmethyl)-1-azoniabicyclo[2.2.2]octane bromide and the following chemical structure:

Umeclidinium bromide is a white powder with a molecular weight of 508.5, and the empirical formula is C29H34NO2•Br (as a quaternary ammonium bromide compound). It is slightly soluble in water.

Vilanterol trifenatate has the chemical name triphenylacetic acid-4-{(1R)-2-[(6-{2-[2,6-dicholorobenzyl)oxy]ethoxy}hexyl)amino]-1-hydroxyethyl}-2-(hydroxymethyl)phenol (1:1) and the following chemical structure:

Vilanterol trifenatate is a white powder with a molecular weight of 774.8, and the empirical formula is C24H33Cl2NO5•C20H16O2. It is practically insoluble in water.

TRELEGY ELLIPTA is a light grey and beige plastic inhaler containing 2 foil blister strips. Each blister on one strip contains a white powder blend of micronized fluticasone furoate (100 or 200 mcg) and lactose monohydrate (12.4 or 12.3 mg) and each blister on the other strip contains a white powder blend of micronized umeclidinium bromide (74.2 mcg equivalent to 62.5 mcg of umeclidinium), micronized vilanterol trifenatate (40 mcg equivalent to 25 mcg of vilanterol), magnesium stearate (75 mcg), and lactose monohydrate (12.3 mg). The lactose monohydrate contains milk proteins. After the inhaler is activated, the powder within both blisters is exposed and ready for dispersion into the airstream created by the patient inhaling through the mouthpiece.

Under standardized in vitro test conditions, TRELEGY ELLIPTA delivers 92 or 184 mcg of fluticasone furoate, 55 mcg of umeclidinium, and 22 mcg of vilanterol per dose when tested at a flow rate of 60 L/min for 4 seconds. At flow rates of 30, 60, and 90 L/min for 4 seconds under in vitro test conditions, TRELEGY ELLIPTA delivers ≥90% of the target dose for each component.

In adult subjects with very severe COPD (FEV1/FVC [forced vital capacity] <70% and FEV1 <30% predicted), mean peak inspiratory flow through the ELLIPTA inhaler was 65.8 L/min (range: 43.5 to 94.1 L/min).

In adult subjects with severe asthma, mean peak inspiratory flow through the ELLIPTA inhaler was 96.6 L/min (range: 72.4 to 124.6 L/min).

The actual amount of drug delivered to the lung will depend on patient factors, such as inspiratory flow profile.

12 CLINICAL PHARMACOLOGY

12.1 Mechanism of Action

TRELEGY ELLIPTA

TRELEGY ELLIPTA contains fluticasone furoate, umeclidinium, and vilanterol. The mechanisms of action described below for the individual components apply to TRELEGY ELLIPTA. These drugs represent 3 different classes of medications (an ICS, an anticholinergic, and a LABA), each having different effects on clinical and physiological indices.

Fluticasone Furoate

Fluticasone furoate is a synthetic trifluorinated corticosteroid with anti-inflammatory activity. Fluticasone furoate has been shown in vitro to exhibit a binding affinity for the human glucocorticoid receptor that is approximately 29.9 times that of dexamethasone and 1.7 times that of fluticasone propionate. The clinical relevance of these findings is unknown.

The precise mechanism through which fluticasone furoate affects COPD and asthma symptoms is not known. Inflammation is an important component in the pathogenesis of COPD and asthma. Corticosteroids have been shown to have a wide range of actions on multiple cell types (e.g., mast cells, eosinophils, neutrophils, macrophages, lymphocytes) and mediators (e.g., histamine, eicosanoids, leukotrienes, cytokines) involved in inflammation. Specific effects of fluticasone furoate demonstrated in in vitro and in vivo models included activation of the glucocorticoid response element, inhibition of pro-inflammatory transcription factors such as NFkB, and inhibition of antigen-induced lung eosinophilia in sensitized rats. These anti-inflammatory actions of corticosteroids may contribute to their efficacy.

Umeclidinium

Umeclidinium is a long-acting muscarinic antagonist, which is often referred to as an anticholinergic. It has similar affinity to the subtypes of muscarinic receptors M1 to M5. In the airways, it exhibits pharmacological effects through inhibition of M3 receptor at the smooth muscle leading to bronchodilation. The competitive and reversible nature of antagonism was shown with human and animal origin receptors and isolated organ preparations. In preclinical in vitro as well as in vivo studies, prevention of methacholine- and acetylcholine-induced bronchoconstrictive effects was dose-dependent and lasted longer than 24 hours. The clinical relevance of these findings is unknown. The bronchodilation following inhalation of umeclidinium is predominantly a site-specific effect.

Vilanterol

Vilanterol is a LABA. In vitro tests have shown the functional selectivity of vilanterol was similar to salmeterol. The clinical relevance of this in vitro finding is unknown.

Although beta2-receptors are the predominant adrenergic receptors in bronchial smooth muscle and beta1-receptors are the predominant receptors in the heart, there are also beta2-receptors in the human heart comprising 10% to 50% of the total beta-adrenergic receptors. The precise function of these receptors has not been established, but they raise the possibility that even highly selective beta2-agonists may have cardiac effects.

The pharmacologic effects of beta2-adrenergic agonist drugs, including vilanterol, are at least in part attributable to stimulation of intracellular adenyl cyclase, the enzyme that catalyzes the conversion of adenosine triphosphate (ATP) to cyclic-3ʹ,5ʹ-adenosine monophosphate (cyclic AMP). Increased cyclic AMP levels cause relaxation of bronchial smooth muscle and inhibition of release of mediators of immediate hypersensitivity from cells, especially from mast cells.

12.2 Pharmacodynamics

Cardiac Electrophysiology

The effect of umeclidinium/vilanterol on cardiac rhythm in subjects diagnosed with COPD was assessed using 24-hour Holter monitoring in 6- and 12-month trials: 53 subjects received umeclidinium/vilanterol 62.5/25 mcg, 281 subjects received umeclidinium/vilanterol 125/25 mcg, and 182 subjects received placebo. No clinically meaningful effects on cardiac rhythm were observed.

The cardiovascular effects from dual combinations of fluticasone furoate/vilanterol and umeclidinium/vilanterol in healthy subjects are presented below.

Fluticasone Furoate/Vilanterol Combination: Healthy Subjects: QTc interval prolongation was studied in a double-blind, multiple-dose, placebo- and positive-controlled crossover study in 85 healthy volunteers. The maximum mean (95% upper confidence bound) difference in QTcF from placebo after baseline correction was 4.9 (7.5) milliseconds and 9.6 (12.2) milliseconds seen 30 minutes after dosing for fluticasone furoate/vilanterol 200/25 mcg and fluticasone furoate/vilanterol 800/100 mcg, respectively.

A dose-dependent increase in heart rate was also observed. The maximum mean (95% upper confidence bound) difference in heart rate from placebo after baseline correction was 7.8 (9.4) beats/min and 17.1 (18.7) beats/min seen 10 minutes after dosing for fluticasone furoate/vilanterol 200/25 mcg and fluticasone furoate/vilanterol 800/100 mcg (8/4 times the recommended dosage), respectively.

Umeclidinium/Vilanterol Combination: Healthy Subjects: QTc interval prolongation was studied in a double-blind, multiple-dose, placebo- and positive-controlled crossover trial in 86 healthy subjects. The maximum mean (95% upper confidence bound) difference in QTcF from placebo after baseline correction was 4.6 (7.1) milliseconds and 8.2 (10.7) milliseconds for umeclidinium/vilanterol 125/25 mcg and umeclidinium/vilanterol 500/100 mcg (8/4 times the recommended dosage), respectively.

A dose-dependent increase in heart rate was also observed. The maximum mean (95% upper confidence bound) difference in heart rate from placebo after baseline correction was 8.8 (10.5) beats/min and 20.5 (22.3) beats/min seen 10 minutes after dosing for umeclidinium/vilanterol 125/25 mcg and umeclidinium/vilanterol 500/100 mcg, respectively.

HPA Axis Effects

Healthy Subjects: Inhaled fluticasone furoate at repeat doses up to 400 mcg was not associated with statistically significant decreases in serum or urinary cortisol in healthy subjects. Decreases in serum and urine cortisol levels were observed at fluticasone furoate exposures several-fold higher than exposures observed at the therapeutic dose.

Subjects with Chronic Obstructive Pulmonary Disease: In a trial with subjects with COPD, treatment with fluticasone furoate (50, 100, or 200 mcg)/vilanterol 25 mcg, vilanterol 25 mcg, or fluticasone furoate (100 or 200 mcg) for 6 months did not affect 24-hour urinary cortisol excretion. A separate trial with subjects with COPD demonstrated no effects on serum cortisol after 28 days of treatment with fluticasone furoate (50, 100, or 200 mcg)/vilanterol 25 mcg.

Subjects with Asthma: A randomized, double-blind, parallel-group trial in 185 subjects with asthma showed no difference between once-daily treatment with fluticasone furoate/vilanterol 100/25 mcg or fluticasone furoate/vilanterol 200/25 mcg compared with placebo on serum cortisol weighted mean (0 to 24 hours), serum cortisol AUC(0-24), and 24-hour urinary cortisol after 6 weeks of treatment, whereas prednisolone 10 mg given once daily for 7 days resulted in significant cortisol suppression.

12.3 Pharmacokinetics

Linear pharmacokinetics was observed for fluticasone furoate (200 to 800 mcg), umeclidinium (62.5 to 500 mcg), and vilanterol (25 to 100 mcg). The pharmacokinetics of fluticasone furoate, umeclidinium, and vilanterol from TRELEGY ELLIPTA are comparable to the pharmacokinetics of fluticasone furoate, umeclidinium, and vilanterol when administered as fluticasone furoate/vilanterol or umeclidinium/vilanterol.

Systemic drug levels [steady-state Cmax and AUC(0-24)] of fluticasone furoate, umeclidinium, and vilanterol following administration of TRELEGY ELLIPTA 100/62.5/25 mcg based on a combined pharmacokinetic dataset from 3 studies in subjects with COPD (N = 821) were within the range of those observed following administration of fluticasone furoate/vilanterol plus umeclidinium administered via 2 inhalers, fluticasone furoate/vilanterol and umeclidinium/vilanterol as the dual combinations, and after administration of fluticasone furoate, umeclidinium, and vilanterol as monotherapy.

Systemic drug levels [steady-state Cmax and AUC(0-24)] of fluticasone furoate, umeclidinium, and vilanterol following administration of TRELEGY ELLIPTA (100/62.5/25 or 200/62.5/25 mcg) based on a population pharmacokinetic analysis from subjects with asthma (1,265 subjects for fluticasone furoate; 634 subjects for umeclidinium; 1,263 subjects for vilanterol) were within the range of those observed following administration of fluticasone furoate/vilanterol as the dual combination when compared with fluticasone furoate 100 and 200 mcg, respectively; the systemic exposure of umeclidinium 62.5 mcg following TRELEGY ELLIPTA (100/62.5/25 or 200/62.5/25 mcg) was within the range of those observed following administration of umeclidinium 62.5 mcg as monotherapy.

The pharmacokinetics of the individual components of TRELEGY ELLIPTA are presented as follows. Plasma levels of fluticasone furoate, umeclidinium, and vilanterol may not predict therapeutic effect.

Absorption

Fluticasone Furoate: Following inhaled administration of fluticasone furoate, Cmax occurred within 0.5 to 1 hour. Absolute bioavailability of fluticasone furoate when administered by inhalation was 15.2%, primarily due to absorption of the inhaled portion of the dose delivered to the lung. Oral bioavailability from the swallowed portion of the dose is low (approximately 1.3%) due to extensive first-pass metabolism. Following repeat dosing of inhaled fluticasone furoate, steady state was achieved within 6 days with up to 2.6-fold accumulation.

Umeclidinium: Following inhaled administration of umeclidinium in healthy subjects, Cmax occurred at 5 to 15 minutes. Umeclidinium is mostly absorbed from the lung after inhaled doses with minimum contribution from oral absorption. Following repeat dosing of inhaled umeclidinium, steady state was achieved within 14 days with up to 1.8-fold accumulation.

Vilanterol: Following inhaled administration of vilanterol in healthy subjects, Cmax occurred at 5 to 15 minutes. Vilanterol is mostly absorbed from the lung after inhaled doses with negligible contribution from oral absorption. Following repeat dosing of inhaled vilanterol, steady state was achieved within 14 days with up to 1.7-fold accumulation.

Distribution

Fluticasone Furoate: Following intravenous administration to healthy subjects, the mean volume of distribution at steady state was 661 L. Binding of fluticasone furoate to human plasma proteins was high (>99%).

Umeclidinium: Following intravenous administration to healthy subjects, the mean volume of distribution was 86 L. In vitro plasma protein binding in human plasma was on average 89%.

Vilanterol: Following intravenous administration to healthy subjects, the mean volume of distribution at steady state was 165 L. In vitro plasma protein binding in human plasma was on average 94%.

Elimination

Metabolism: Fluticasone Furoate: Fluticasone furoate is cleared from systemic circulation principally by hepatic metabolism via CYP3A4 to metabolites with significantly reduced corticosteroid activity. There was no in vivo evidence for cleavage of the furoate moiety resulting in the formation of fluticasone.

Umeclidinium: In vitro data showed that umeclidinium is primarily metabolized by the enzyme cytochrome P450 2D6 (CYP2D6) and is a substrate for the P-glycoprotein (P-gp) transporter. The primary metabolic routes for umeclidinium are oxidative (hydroxylation, O-dealkylation) followed by conjugation (e.g., glucuronidation), resulting in a range of metabolites with either reduced pharmacological activity or for which the pharmacological activity has not been established. Systemic exposure to the metabolites is low.

Vilanterol: In vitro data showed that vilanterol is metabolized principally by CYP3A4 and is a substrate for the P-gp transporter. Vilanterol is metabolized to a range of metabolites with significantly reduced β1- and β2-agonist activity.

Excretion: Fluticasone Furoate: The plasma elimination half-life following repeat-dose inhaled administration averaged 24 hours. Following intravenous dosing with radiolabeled fluticasone furoate, mass balance showed 90% of the radiolabel in the feces and 2% in the urine. Following oral dosing, radiolabel recovered in feces was 101% of the total dose and that in urine was approximately 1% of the total dose.

Umeclidinium: The effective half-life after once-daily oral dosing is 11 hours. Following intravenous dosing with radiolabeled umeclidinium, mass balance showed 58% of the radiolabel in the feces and 22% in the urine. The excretion of the drug-related material in the feces following intravenous dosing indicated elimination in the bile. Following oral dosing to healthy male subjects, radiolabel recovered in feces was 92% of the total dose and that in urine was <1% of the total dose, suggesting negligible oral absorption.

Vilanterol: The effective half-life for vilanterol, as determined from inhalation administration of multiple doses, is 11 hours. Following oral administration of radiolabeled vilanterol, mass balance showed 70% of the radiolabel in the urine and 30% in the feces.

Specific Populations

The effects of intrinsic and extrinsic factors on the pharmacokinetics of fluticasone furoate, umeclidinium, and vilanterol are shown in Figures 1, 2, 3, and 4. Based on population pharmacokinetic analyses in COPD and asthma, none of the covariates assessed (i.e., age, race, gender) had a clinically relevant effect on fluticasone furoate, umeclidinium, or vilanterol pharmacokinetics when administered as TRELEGY ELLIPTA.

Figure 1. Impact of Intrinsic Factors on the Pharmacokinetics (PK) of Fluticasone Furoate (FF), Umeclidinium (UMEC), and Vilanterol (VI) following Coadministration in COPD

Figure 2. Impact of Intrinsic Factors on the Pharmacokinetics (PK) of Fluticasone Furoate (FF), Umeclidinium (UMEC), and Vilanterol (VI) following Coadministration in Asthmaa

a Age, ethnicity, and gender comparison for TRELEGY ELLIPTA 200/62.5/25 mcg in subjects with asthma.

Figure 3. Impact of Intrinsic Factorsa and Coadministered Drugsb on the Pharmacokinetics (PK) of Fluticasone Furoate (FF) and Vilanterol (VI) following Administration as Fluticasone Furoate/Vilanterol Combination or following Vilanterol Coadministered with Umeclidinium

a Renal groups (fluticasone furoate/vilanterol 200/25 mcg) and hepatic groups (fluticasone furoate/vilanterol 200/25 mcg or fluticasone furoate/vilanterol 100/12.5 mcg).

b Compared with placebo group.

Figure 4. Impact of Intrinsic Factors and Coadministered Drugs on the Systemic Exposure of Umeclidinium

Racial or Ethnic Groups: Fluticasone Furoate: Systemic exposure [AUC(0-24)] to inhaled fluticasone furoate was approximately 30% higher in subjects with COPD of East Asian heritage (n = 113) compared with White subjects (Figure 1). However, this higher exposure to fluticasone furoate is not expected to have clinically relevant effects on serum or urine cortisol or on efficacy in these racial groups. In East Asian subjects with asthma (Japanese, East Asian, and Southeast Asian heritage) (n = 92), there was no effect of race on pharmacokinetics of fluticasone furoate (Figure 2).

Umeclidinium: There was no effect of race on the pharmacokinetics of umeclidinium in subjects with COPD or asthma (Figures 1 and 2).

Vilanterol: There was no effect of race on the pharmacokinetics of vilanterol in subjects with COPD (Figure 1). In East Asian subjects with asthma (Japanese, East Asian, and Southeast Asian heritage) (n = 92), estimates of vilanterol Cmax at steady state were approximately 3-fold higher than non-East Asian subjects (Figure 2). However, the higher systemic exposure is not expected to have a clinically relevant effect on heart rate.

Patients with Hepatic Impairment: Fluticasone Furoate: Following repeat dosing of fluticasone furoate/vilanterol 200/25 mcg (100/12.5 mcg in the severe impairment group) for 7 days, there was an increase of 34%, 83%, and 75% in fluticasone furoate systemic exposure (AUC) in subjects with mild, moderate, and severe hepatic impairment, respectively, compared with healthy subjects (Figure 3).

In subjects with moderate hepatic impairment receiving fluticasone furoate/vilanterol 200/25 mcg, mean serum cortisol (0 to 24 hours) was reduced by 34% (90% CI: 11%, 51%) compared with healthy subjects. In subjects with severe hepatic impairment receiving fluticasone furoate/vilanterol 100/12.5 mcg, mean serum cortisol (0 to 24 hours) was increased by 14% (90% CI: -16%, 55%) compared with healthy subjects. Patients with moderate to severe hepatic disease should be closely monitored.

Umeclidinium: The impact of hepatic impairment on the pharmacokinetics of umeclidinium has been evaluated in subjects with moderate hepatic impairment (Child-Pugh score of 7-9). There was no evidence of an increase in systemic exposure to umeclidinium (Cmax and AUC) (Figure 4). There was no evidence of altered protein binding in subjects with moderate hepatic impairment compared with healthy subjects. TRELEGY ELLIPTA has not been evaluated in subjects with severe hepatic impairment.

Vilanterol: Hepatic impairment had no effect on vilanterol systemic exposure (Cmax and AUCss on Day 7) following repeat-dose administration of fluticasone furoate/vilanterol 200/25 mcg (100/12.5 mcg in the severe impairment group) for 7 days (Figure 3).

There were no additional clinically relevant effects of the fluticasone furoate/vilanterol combinations on heart rate or serum potassium in subjects with mild or moderate hepatic impairment (vilanterol 25 mcg combination) or with severe hepatic impairment (vilanterol 12.5 mcg combination) compared with healthy subjects.

Patients with Renal Impairment: Fluticasone Furoate: Systemic exposure was not increased in subjects with severe renal impairment compared with healthy subjects (Figure 3). There was no evidence of greater corticosteroid class-related systemic effects (assessed by serum cortisol) in subjects with severe renal impairment compared with healthy subjects.

Umeclidinium: The pharmacokinetics of umeclidinium has been evaluated in subjects with severe renal impairment (CrCl <30 mL/min). There was no evidence of an increase in systemic exposure to umeclidinium (Cmax and AUC) (Figure 4). There was no evidence of altered protein binding in subjects with severe renal impairment compared with healthy subjects.

Vilanterol: Systemic exposure (AUCss) was 56% higher in subjects with severe renal impairment compared with healthy subjects (Figure 3). There was no evidence of greater beta‑agonist class-related systemic effects (assessed by heart rate and serum potassium) in subjects with severe renal impairment compared with healthy subjects.

Drug Interaction Studies

No drug-drug interaction studies have been conducted with TRELEGY ELLIPTA. The information below is from drug-drug interaction studies conducted with umeclidinium, fluticasone furoate/vilanterol, or umeclidinium/vilanterol. The potential for fluticasone furoate, umeclidinium, and vilanterol to inhibit or induce metabolic enzymes and transporter systems is negligible at low inhalation doses.

Inhibitors of Cytochrome P450 3A4: The exposure (AUC) of fluticasone furoate and vilanterol were 36% and 65% higher, respectively, when coadministered with ketoconazole 400 mg compared with placebo (Figure 3). The increase in fluticasone furoate exposure was associated with a 27% reduction in weighted mean serum cortisol (0 to 24 hours). The increase in vilanterol exposure was not associated with an increase in beta-agonist–related systemic effects on heart rate or blood potassium.

Cytochrome P450 2D6: In vitro metabolism of umeclidinium is mediated primarily by CYP2D6. However, no clinically meaningful difference in systemic exposure to umeclidinium (500 mcg) (8 times the approved dose) was observed following repeat daily inhaled dosing to normal (ultra‑rapid, extensive, and intermediate metabolizers) and CYP2D6 poor metabolizer subjects.

Inhibitors of P-glycoprotein: Fluticasone furoate, umeclidinium, and vilanterol are substrates of P‑gp. Coadministration of repeat-dose (240 mg once daily) verapamil (a moderate CYP3A4 inhibitor and a P-gp inhibitor) did not affect the vilanterol Cmax or AUC in healthy subjects (Figure 3). Drug interaction trials with a specific P-gp inhibitor and fluticasone furoate have not been conducted. The effect of the moderate P-gp transporter inhibitor verapamil (240 mg once daily) on the steady-state pharmacokinetics of umeclidinium was assessed in healthy subjects. No effect on umeclidinium Cmax was observed; however, an approximately 1.4-fold increase in umeclidinium AUC was observed (Figure 4).

13 NONCLINICAL TOXICOLOGY

13.1 Carcinogenesis, Mutagenesis, Impairment of Fertility

TRELEGY ELLIPTA

No studies of carcinogenicity, mutagenicity, or impairment of fertility were conducted with TRELEGY ELLIPTA; however, studies are available for the individual components, fluticasone furoate, umeclidinium, and vilanterol, as described below.

Fluticasone Furoate

Fluticasone furoate produced no treatment-related increases in the incidence of tumors in 2-year inhalation studies in rats and mice at inhaled doses up to 9 and 19 mcg/kg/day, respectively (both approximately 0.5 times the MRHDID of 200 mcg for adults on a mcg/m^2 basis).

Fluticasone furoate did not induce gene mutation in bacteria or chromosomal damage in a mammalian cell mutation test in mouse lymphoma L5178Y cells in vitro. There was also no evidence of genotoxicity in the in vivo micronucleus test in rats.

No evidence of impairment of fertility was observed in male and female rats at inhaled fluticasone furoate doses up to 29 and 91 mcg/kg/day, respectively (approximately 3 and 8 times, respectively, the MRHDID of 200 mcg for adults on an AUC basis).

Umeclidinium

Umeclidinium produced no treatment-related increases in the incidence of tumors in 2-year inhalation studies in rats and mice at inhaled doses up to 137 and 295/200 mcg/kg/day (male/female), respectively (approximately 17 and 20/20 times, respectively, the MRHDID for adults on an AUC basis).

Umeclidinium tested negative in the following genotoxicity assays: the in vitro Ames assay, in vitro mouse lymphoma assay, and in vivo rat bone marrow micronucleus assay.

No evidence of impairment of fertility was observed in male and female rats at subcutaneous doses up to 180 mcg/kg/day and at inhaled doses up to 294 mcg/kg/day, respectively (approximately 60 and 40 times, respectively, the MRHDID for adults on an AUC basis).

Vilanterol

In a 2-year carcinogenicity study in mice, vilanterol caused a statistically significant increase in ovarian tubulostromal adenomas in females at an inhaled dose of 29,500 mcg/kg/day (approximately 9,920 times the MRHDID for adults on an AUC basis). No increase in tumors was seen at an inhaled dose of 615 mcg/kg/day (approximately 370 times the MRHDID for adults on an AUC basis).

In a 2-year carcinogenicity study in rats, vilanterol caused statistically significant increases in mesovarian leiomyomas in females and shortening of the latency of pituitary tumors at inhaled doses greater than or equal to 84.4 mcg/kg/day (greater than or equal to approximately 25 times the MRHDID for adults on an AUC basis). No tumors were seen at an inhalation dose of 10.5 mcg/kg/day (approximately equal to the MRHDID for adults on an AUC basis).

These tumor findings in rodents are similar to those reported previously for other beta-adrenergic agonist drugs. The relevance of these findings to human use is unknown.

Vilanterol tested negative in the following genotoxicity assays: the in vitro Ames assay, in vivo rat bone marrow micronucleus assay, in vivo rat unscheduled DNA synthesis (UDS) assay, and in vitro Syrian hamster embryo (SHE) cell assay. Vilanterol tested equivocal in the in vitro mouse lymphoma assay.

No evidence of impairment of fertility was observed in male and female rats at inhaled vilanterol doses up to 31,500 and 37,100 mcg/kg/day, respectively (both approximately 4,090 times the MRHDID based on AUC).

14 CLINICAL STUDIES

14.1 Chronic Obstructive Pulmonary Disease

The clinical efficacy of TRELEGY ELLIPTA has been evaluated in 3 clinical trials in subjects with COPD, including chronic bronchitis and/or emphysema: Trial 1 (NCT01957163), Trial 2 (NCT02119286), and Trial 3 (NCT02164513).

Trials 1 and 2 were multicenter, randomized, double-blind, parallel-group, 12-week treatment trials in subjects with COPD. Across both trials, a total of 412 subjects received coadministration of umeclidinium 62.5 mcg + fluticasone furoate/vilanterol 100/25 mcg, the components of TRELEGY ELLIPTA. Comparative in vitro data (drug delivery and aerodynamic particle size distribution) provide support for reliance on coadministration studies with umeclidinium 62.5 mcg + fluticasone furoate/vilanterol 100/25 mcg. These data demonstrated no pharmaceutical interactions and that each drug component (fluticasone furoate, umeclidinium, and vilanterol) was delivered in a comparable manner whether administered via a single ELLIPTA inhaler or from separate inhalers.

The population demographics for Trials 1 and 2 were: mean age of 64 years, 92% White, 66% male, and an average smoking history of 48 pack-years, with 50% identified as current smokers. At screening, the mean postbronchodilator percent predicted FEV1 was 46% (range: 14% to 76%), the mean postbronchodilator FEV1/FVC ratio was 0.48 (range: 0.21 to 0.70), and the mean percent reversibility was 13% (range: -24% to 86%).

Trial 3 was a randomized, multicenter, double-blind, parallel-group, 52-week treatment trial comparing the clinical efficacy of TRELEGY ELLIPTA 100/62.5/25 mcg with the fixed-dose combinations of fluticasone furoate/vilanterol 100/25 mcg and umeclidinium/vilanterol 62.5/25 mcg. A total of 10,355 subjects with COPD with a history of 1 or more moderate or severe exacerbations in the prior 12 months were randomized (2:2:1) to receive TRELEGY ELLIPTA, fluticasone furoate/vilanterol, or umeclidinium/vilanterol administered once daily.

The population demographics across all treatments were: mean age of 65 years, 77% White, 66% male, and an average smoking history of 46.6 pack-years, with 35% identified as current smokers. At study entry, the most common COPD medications were ICS + anticholinergic + LABA (34%), ICS + LABA (26%), anticholinergic + LABA (8%), and anticholinergic (7%); the mean postbronchodilator percent predicted FEV1 was 46% (SD: 15%), the mean postbronchodilator FEV1/FVC ratio was 0.47 (SD: 0.12), and the mean percent reversibility was 10% (range: -59% to 125%).

Lung Function: In Trials 1 and 2, the primary endpoint was change from baseline in trough (predose) FEV1 at Day 85 (defined as the mean of the FEV1 values obtained at 23 and 24 hours after the previous dose on Day 84). For both COPD trials, umeclidinium + fluticasone furoate/vilanterol demonstrated a statistically significant increase relative to placebo + fluticasone furoate/vilanterol (Table 4); similar results were demonstrated for the secondary endpoint of the weighted mean FEV1 (0 to 6 hours postdose) on Day 84 (Table 4).

Table 4. Least Squares Mean Change from Baseline in Trough FEV1 and Weighted Mean FEV1 (0-6 h) at Week 12 (Days 84/85)
Treatment | n | Trough FEV1 (mL)a | Weighted Mean FEV1 (0-6 h) (mL)b
Treatment | n | Difference from Placebo + FF/VI; (95% CI) | Difference from Placebo + FF/VI; (95% CI)
Trial 1
UMEC + FF/VI | 206 | 124 | 153
 |  | (93, 154) | (118, 187)
Trial 2
UMEC + FF/VI | 206 | 122 | 147
 |  | (91, 152) | (114, 179)
FEV1 = Forced Expiratory Volume in 1 Second, FF/VI = Fluticasone Furoate/Vilanterol 100/25 mcg, UMEC = Umeclidinium 62.5 mcg.
a At Day 85.
b At Day 84.
c For Placebo + FF/VI: Trial 1, n = 206; Trial 2, n = 206.

Greater least squares (LS) mean changes from baseline in FEV1 over time were demonstrated for the umeclidinium + fluticasone furoate/vilanterol treatment group compared with the placebo + fluticasone furoate/vilanterol treatment group starting at 15 minutes postdose on Day 1. For Trial 1, LS mean changes in FEV1 over time relative to baseline are displayed for Day 1 and Day 84 in Figures 5 and 6, respectively. Similar results were seen in Trial 2.

Figure 5. Least Squares (LS) Mean Change from Baseline in Postdose Serial FEV1 (mL) on Day 1

Figure 6. Least Squares (LS) Mean Change from Baseline in Postdose Serial FEV1 (mL) on Day 84

In Trial 3, treatment with TRELEGY ELLIPTA 100/62.5/25 mcg demonstrated a statistically significant improvement in lung function (mean change from baseline trough FEV1 at Week 52) compared with fluticasone furoate/vilanterol and umeclidinium/vilanterol. The mean change from baseline in trough (predose) FEV1 at Week 52 was 97 mL for TRELEGY ELLIPTA compared with fluticasone furoate/vilanterol (95% CI: 85, 109; P<0.001) and 54 mL for TRELEGY ELLIPTA compared with umeclidinium/vilanterol (95% CI: 39, 69; P<0.001). The effects on lung function (mean change from baseline trough FEV1) of TRELEGY ELLIPTA compared with fluticasone furoate/vilanterol and umeclidinium/vilanterol were observed at all timepoints over the course of the 52-week study (Figure 7).

Figure 7. Least Squares (LS) Mean Change from Baseline in Trough FEV1 (mL)

Exacerbations: In Trial 3, the primary endpoint was annual rate of on-treatment moderate and severe exacerbations in subjects with COPD treated with TRELEGY ELLIPTA 100/62.5/25 mcg compared with fluticasone furoate/vilanterol and umeclidinium/vilanterol. Exacerbations were defined as worsening of 2 or more major symptoms (dyspnea, sputum volume, and sputum purulence) or worsening of any 1 major symptom together with any 1 of the following minor symptoms: sore throat, colds (nasal discharge and/or nasal congestion), fever without other cause, and increased cough or wheeze for at least 2 consecutive days. Exacerbations were considered to be moderate severity if treatment with systemic corticosteroids and/or antibiotics was required and were considered to be severe if resulted in hospitalization or death.

Treatment with TRELEGY ELLIPTA statistically significantly reduced the on-treatment annual rate of moderate/severe exacerbations by 15% compared with fluticasone furoate/vilanterol and by 25% compared with umeclidinium/vilanterol (Table 5).

Table 5. Moderate and Severe Chronic Obstructive Pulmonary Disease Exacerbations (Trial 3)a
Treatment | n | Mean Annual Rate; (exacerbations/y) | Rate Ratio vs. Comparator; (95% CI) | % Reduction in Exacerbation Rate; (95% CI) | P Value
TRELEGY ELLIPTA | 4,145 | 0.91
FF/VI | 4,133 | 1.07 | 0.85; (0.80, 0.90) | 15; (10, 20) | P<0.001
UMEC/VI | 2,069 | 1.21 | 0.75; (0.70, 0.81) | 25; (19, 30) | P<0.001
FF/VI = Fluticasone furoate/vilanterol 100/25 mcg, UMEC/VI = Umeclidinium/vilanterol 62.5/25 mcg.
a On-treatment analyses excluded exacerbation data collected after discontinuation of study treatment.

Treatment with TRELEGY ELLIPTA statistically significantly decreased the risk of a moderate/severe COPD exacerbation as measured by time to first exacerbation when compared with fluticasone furoate/vilanterol (14.8%; 95% CI: 9.3, 19.9; P<0.001) and umeclidinium/vilanterol (16.0%; 95% CI: 9.4, 22.1; P<0.001).

Treatment with TRELEGY ELLIPTA reduced the on-treatment annual rate of severe COPD exacerbations (i.e., requiring hospitalization or resulting in death) by 13% compared with fluticasone furoate/vilanterol (95% CI: -1, 24; P = 0.064) which was not statistically significant. Treatment with TRELEGY ELLIPTA statistically significantly reduced the on-treatment annual rate of severe COPD exacerbations by 34% compared with umeclidinium/vilanterol (95% CI: 22, 44; P<0.001).

Health-Related Quality of Life: In all 3 trials, health-related quality of life was assessed using the St. George’s Respiratory Questionnaire for COPD patients (SGRQ-C), a disease-specific shorter version derived from the original St. George’s Respiratory Questionnaire (SGRQ). Results were transformed to the SGRQ for reporting purposes. In Trial 1, the on-treatment responder rate at Week 12 (response defined as a decrease in score from baseline of 4 or more) was 40% for umeclidinium +fluticasone furoate/vilanterol vs. 35% for placebo + fluticasone furoate/vilanterol [odds ratio (OR): 1.2; 95% CI: 0.8, 1.8]. In Trial 2, the on-treatment responder rate at Week 12 was 35% for umeclidinium + fluticasone furoate/vilanterol vs. 21% for placebo + fluticasone furoate/vilanterol (OR: 2.0; 95% CI: 1.3, 3.1). In Trial 3, the on-treatment responder rate at Week 52 was statistically significantly greater for subjects treated with TRELEGY ELLIPTA (42%) compared with fluticasone furoate/vilanterol (34%; OR: 1.41; 95% CI: 1.29, 1.55; P<0.001) and compared with umeclidinium/vilanterol (34%; OR: 1.41; 95% CI: 1.26, 1.57; P<0.001).

Other Endpoints: In Trials 1 and 2, subjects treated with umeclidinium + fluticasone furoate/vilanterol on average used less rescue medication compared with subjects treated with placebo + fluticasone furoate/vilanterol over Weeks 1 to 12. In Trial 3, subjects treated with TRELEGY ELLIPTA on average used less rescue medication (mean number of uses per day and percentage of rescue-free 24-hour periods) compared with subjects treated with fluticasone furoate/vilanterol or umeclidinium/vilanterol over the course of the 52-week study.

14.2 Asthma

The safety and efficacy of TRELEGY ELLIPTA were evaluated in 2,436 subjects in a randomized, double-blind, parallel-group, active-controlled confirmatory trial of 24 to 52 weeks’ duration in adult subjects with asthma inadequately controlled on their current treatments of combination therapy (ICS plus a LABA) (Trial 4, NCT02924688).

Subjects with an Asthma Control Questionnaire (ACQ-6) score ≥1.5 on their current asthma treatment of ICS (greater than fluticasone propionate 250 mcg/day or equivalent) plus LABA entered a 3-week run-in period of treatment with fluticasone propionate/salmeterol 250/50 mcg twice daily. Subjects who remained inadequately controlled (ACQ-6 ≥1.5) after the run-in period were transferred to fluticasone furoate/vilanterol 100/25 mcg once daily for a 2-week stabilization period. After the 5-week run-in/stabilization period, eligible subjects were randomized to receive once-daily inhalations of TRELEGY ELLIPTA 100/62.5/25 mcg (n = 406), TRELEGY ELLIPTA 200/62.5/25 mcg (n = 408), fluticasone furoate/umeclidinium/vilanterol 100/31.25 mcg/25 mcg (n = 405), fluticasone furoate/umeclidinium/vilanterol 200/31.25 mcg/25 mcg (n = 404), fluticasone furoate/vilanterol 100/25 mcg (n = 407), or fluticasone furoate/vilanterol 200/25 mcg (n = 406).

Across all treatment groups, baseline demographics were similar. The majority of subjects were female (62%), White (80%), and had never smoked (81%), with a mean age of 53 years and mean asthma duration of 21 years (range: 1 to 70). The trial excluded current smokers; past smokers had an average smoking history of 4.3 pack-years. In the prior 12 months, 85% of subjects reported having any exacerbation; approximately 63% of subjects reported having an exacerbation that required oral/systemic corticosteroids and/or hospitalization.

At screening, the mean prebronchodilator percent predicted FEV1 was 58.5% (SD: 12.8%); the mean percent reversibility was 29.9% (SD: 18.1%), with a mean absolute reversibility of 484 mL (SD: 274 mL), and the mean ACQ-6 score was 2.5 (SD: 0.6). During the 5-week run‑in/stabilization period, subjects had improvements in both lung function (trough FEV1 improvement of 287 mL) and asthma control (mean ACQ-6 score decreased by 0.6). At randomization, the majority (93%) remained not well controlled (mean ACQ-6 score of 1.9) and the mean prebronchodilator percent predicted FEV1 was 68.2% (SD: 14.8%).

Lung Function: The primary efficacy endpoint was change from baseline in trough FEV1 at Week 24. Both TRELEGY ELLIPTA 100/62.5/25 mcg and TRELEGY ELLIPTA 200/62.5/25 mcg showed statistically significant improvements in lung function compared with fluticasone furoate/vilanterol 100/25 mcg and fluticasone furoate/vilanterol 200/25 mcg, respectively (Table 6, Figures 8 and 9).

Table 6. Least Squares Mean Change from Baseline in Trough FEV1 at Week 24
Trough FEV1 (mL) | FF/VI; 100/25 mcg; (n = 407) | TRELEGY ELLIPTA; 100/62.5/25 mcg; (n = 406) | FF/VI; 200/25 mcg; (n = 406) | TRELEGY ELLIPTA; 200/62.5/25 mcg; (n = 408)
Least squares mean | 2,048 | 2,157 | 2,099 | 2,191
Least squares mean change (SE) | 24 (15.7) | 134 (15.5) | 76 (15.6) | 168 (15.5)
TRELEGY ELLIPTA 100/62.5/25 mcg vs. FF/VI 100/25 mcg
Difference | Reference | 110 | –– | ––
95% CI |  | 66, 153
P value |  | P<0.001
TRELEGY ELLIPTA 200/62.5/25 mcg vs. FF/VI 200/25 mcg
Difference | –– | –– | Reference | 92
95% CI |  |  |  | 49, 135
P value |  |  |  | P<0.001
FEV1 = Forced Expiratory Volume in 1 Second, FF/VI = Fluticasone Furoate/Vilanterol.

Figure 8. Least Squares Mean Change from Baseline in Trough FEV1 (mL) with TRELEGY ELLIPTA 100/62.5/25 mcg over 24 Weeks of Treatment

Figure 9. Least Squares Mean Change from Baseline in Trough FEV1 (mL) with TRELEGY ELLIPTA 200/62.5/25 mcg over 24 Weeks of Treatment

The difference in change from baseline in trough FEV1 at Week 24 for TRELEGY ELLIPTA 100/62.5/25 mcg compared with fluticasone furoate/vilanterol 200/25 mcg was 59 mL (95% CI: 15, 102).

The change from baseline in FEV1 at 3 hours post-dose was supportive of the primary endpoint with improvements for TRELEGY ELLIPTA 100/62.5/25 mcg compared with fluticasone furoate/vilanterol 100/25 mcg (111 mL, 95% CI: 67, 155) and TRELEGY ELLIPTA 200/62.5/25 mcg compared with fluticasone furoate/vilanterol 200/25 mcg (118 mL, 95% CI: 74, 162).

Onset of action was determined in a separate trial conducted with fluticasone furoate/vilanterol; the median time to onset (defined as a 100-mL increase from baseline in mean FEV1) was approximately 15 minutes.

Additional bronchodilator effects of umeclidinium in TRELEGY ELLIPTA compared with fluticasone furoate/vilanterol were present over the 24-hour dosing period as shown by 3 hours post-dose FEV1, PM FEV1, and trough FEV1 endpoints. The bronchodilator effects of TRELEGY ELLIPTA were consistently observed from Week 1 through Week 24.

Exacerbations: Asthma exacerbations were assessed over the 52-week treatment period. Asthma exacerbations were defined as deterioration of asthma requiring the use of systemic corticosteroid (or at least a doubling of maintenance dose) for at least 3 days or an inpatient hospitalization or emergency department visit due to asthma that required systemic corticosteroid.

In a descriptive pooled analysis, the mean annualized rate of exacerbations was 0.31 for TRELEGY ELLIPTA [100/62.5/25 and 200/62.5/25 mcg, 127 of 814 (16%) patients reported exacerbations] and 0.31 for fluticasone furoate/vilanterol [100/25 and 200/25 mcg, 132 of 813 (16%) patients reported exacerbations] (2.6% reduction in rate; 95% CI: -26.2, 24.9).

In descriptive unpooled analyses, the mean annualized rates of exacerbations were 0.41 and 0.23 for TRELEGY ELLIPTA 100/62.5/25 mcg and TRELEGY ELLIPTA 200/62.5/25 mcg, respectively. The mean annualized rates of exacerbations were 0.38 and 0.26 for fluticasone furoate/vilanterol 100/25 mcg and fluticasone furoate/vilanterol 200/25 mcg, respectively.

Health-Related Quality of Life: Additional efficacy measures included Asthma Control Questionnaire (ACQ). The ACQ-7 incorporates 5 questions on symptoms, FEV1, and rescue bronchodilator use and was assessed at Week 24. ACQ-7 (7-items) responder was defined as a decrease in score of ≥0.5.

In a descriptive pooled analysis, the ACQ-7 responder rate was 63% for TRELEGY ELLIPTA (100/62.5/25 and 200/62.5/25 mcg) compared with 55% for fluticasone furoate/vilanterol (100/25 and 200/25 mcg) at Week 24, favoring TRELEGY ELLIPTA (OR: 1.43; 95% CI: 1.16, 1.76).

In an unpooled descriptive analysis, the ACQ-7 responder rate was 62% for TRELEGY ELLIPTA 100/62.5/25 mcg compared with 52% for fluticasone furoate/vilanterol 100/25 mcg (OR: 1.59; 95% CI: 1.18, 2.13) at Week 24, favoring TRELEGY ELLIPTA. The ACQ-7 responder rate was 64% for TRELEGY ELLIPTA 200/62.5/25 mcg compared with 58% for fluticasone furoate/vilanterol 200/25 mcg (OR: 1.28; 95% CI: 0.95, 1.72) at Week 24, favoring TRELEGY ELLIPTA.

The ACQ-5 (comprising the 5 questions on symptoms from ACQ-7) responder rates at Week 24 for pooled and unpooled analyses were similar to the ACQ-7 results.

16 HOW SUPPLIED/STORAGE AND HANDLING

TRELEGY ELLIPTA is supplied as a disposable light grey and beige plastic inhaler containing 2 foil strips, each with 30 blisters (or 14 blisters for the institutional pack).

One strip contains fluticasone furoate (100 or 200 mcg per blister), and the other strip contains a blend of umeclidinium and vilanterol (62.5 and 25 mcg per blister, respectively).

A blister from each strip is used to create 1 dose. The inhaler is packaged within a moisture-protective foil tray with a desiccant and a peelable lid in the following packs:

NDC 0173-0887-10 TRELEGY ELLIPTA 100/62.5/25 mcg 30 inhalations (60 blisters)

NDC 0173-0887-14 TRELEGY ELLIPTA 100/62.5/25 mcg 14 inhalations (28 blisters), institutional pack

NDC 0173-0893-10 TRELEGY ELLIPTA 200/62.5/25 mcg 30 inhalations (60 blisters)

NDC 0173-0893-14 TRELEGY ELLIPTA 200/62.5/25 mcg 14 inhalations (28 blisters), institutional pack

Store at room temperature between 68°F and 77°F (20°C and 25°C); excursions permitted from 59°F to 86°F (15°C to 30°C) [See USP Controlled Room Temperature]. Store in a dry place away from direct heat or sunlight. Keep out of reach of children.

TRELEGY ELLIPTA should be stored inside the unopened moisture-protective foil tray and only removed from the tray immediately before initial use. Discard TRELEGY ELLIPTA 6 weeks after opening the foil tray or when the counter reads “0” (after all blisters have been used), whichever comes first. The inhaler is not reusable. Do not attempt to take the inhaler apart.

17 PATIENT COUNSELING INFORMATION

Advise the patient to read the FDA-approved patient labeling (Patient Information and Instructions for Use).

Serious Asthma-Related Events

Inform patients with asthma that LABA when used alone increases the risk of asthma-related hospitalization or asthma-related death. Available data show that when ICS and LABA are used together, such as with TRELEGY ELLIPTA, there is not a significant increase in the risk of these events. [See Warnings and Precautions (5.1).]

Not for Acute Symptoms

Inform patients that TRELEGY ELLIPTA is not meant to relieve acute symptoms of COPD or asthma and extra doses should not be used for that purpose. Advise patients to treat acute symptoms with an inhaled, short-acting beta2-agonist such as albuterol. Provide patients with such medication and instruct them in how it should be used.

Instruct patients to seek medical attention immediately if they experience any of the following:

- Decreasing effectiveness of inhaled, short-acting beta2-agonists
- Need for more inhalations than usual of inhaled, short-acting beta2-agonists
- Significant decrease in lung function as outlined by the physician

Tell patients they should not stop therapy with TRELEGY ELLIPTA without physician/provider guidance since symptoms may recur after discontinuation. [See Warnings and Precautions (5.2).]

Do Not Use Additional Long-acting Beta2-agonists

Instruct patients not to use other LABA for COPD and asthma. [See Warnings and Precautions (5.3).]

Oropharyngeal Candidiasis

Inform patients that localized infections with Candida albicans occurred in the mouth and pharynx in some patients. If oropharyngeal candidiasis develops, treat it with appropriate local or systemic (i.e., oral) antifungal therapy while still continuing therapy with TRELEGY ELLIPTA, but at times therapy with TRELEGY ELLIPTA may need to be temporarily interrupted under close medical supervision. Advise patients to rinse the mouth with water without swallowing after inhalation to help reduce the risk of thrush. [See Warnings and Precautions (5.4).]

Pneumonia

Patients with COPD have a higher risk of pneumonia; instruct them to contact their healthcare providers if they develop symptoms of pneumonia. [See Warnings and Precautions (5.5).]

Immunosuppression and Risk of Infections

Warn patients who are on immunosuppressant doses of corticosteroids to avoid exposure to chickenpox or measles and, if exposed, to consult their physicians without delay. Inform patients of potential worsening of existing tuberculosis; fungal, bacterial, viral, or parasitic infections; or ocular herpes simplex. [See Warnings and Precautions (5.6).]

Hypercorticism and Adrenal Suppression

Advise patients that TRELEGY ELLIPTA may cause systemic corticosteroid effects of hypercorticism and adrenal suppression. Additionally, inform patients that deaths due to adrenal insufficiency have occurred during and after transfer from systemic corticosteroids. Patients should taper slowly from systemic corticosteroids if transferring to TRELEGY ELLIPTA. [See Warnings and Precautions (5.8).]

Paradoxical Bronchospasm

As with other inhaled medicines, TRELEGY ELLIPTA can cause paradoxical bronchospasm. If paradoxical bronchospasm occurs, instruct patients to discontinue TRELEGY ELLIPTA and contact their healthcare provider right away. [See Warnings and Precautions (5.10).]

Hypersensitivity Reactions, including Anaphylaxis

Advise patients that hypersensitivity reactions (e.g., anaphylaxis, angioedema, rash, urticaria) may occur after administration of TRELEGY ELLIPTA. Instruct patients to discontinue TRELEGY ELLIPTA if such reactions occur. There have been reports of anaphylactic reactions in patients with severe milk protein allergy after inhalation of other powder medications containing lactose; therefore, patients with severe milk protein allergy should not use TRELEGY ELLIPTA. [See Warnings and Precautions (5.11).]

Reduction in Bone Mineral Density

Advise patients who are at an increased risk for decreased BMD that the use of corticosteroids may pose an additional risk. [See Warnings and Precautions (5.13).]

Glaucoma and Cataracts

Advise patients that long-term use of ICS may increase the risk of some eye problems (cataracts or glaucoma); consider regular eye examinations.

Instruct patients to be alert for signs and symptoms of acute narrow-angle glaucoma (e.g., eye pain or discomfort, blurred vision, visual halos or colored images in association with red eyes from conjunctival congestion and corneal edema). Instruct patients to consult a physician immediately if any of these signs or symptoms develop. [See Warnings and Precautions (5.14).]

Worsening of Urinary Retention

Instruct patients to be alert for signs and symptoms of urinary retention (e.g., difficulty passing urine, painful urination). Instruct patients to consult a physician immediately if any of these signs or symptoms develop. [See Warnings and Precautions (5.15).]

Risks Associated with Beta-agonist Therapy

Inform patients of adverse effects associated with beta2-agonists, such as palpitations, chest pain, rapid heart rate, tremor, or nervousness. Instruct patients to consult a health care practitioner immediately should any of these signs and symptoms develop. [See Warnings and Precautions (5.12).]

Trademarks are owned by or licensed to the GSK group of companies.

GlaxoSmithKline

Durham, NC 27701

©2023 GSK group of companies or its licensor.

TRL:9PI

PATIENT INFORMATION

TRELEGY ELLIPTA (TREL-e-ge e-LIP-ta)

(fluticasone furoate, umeclidinium, and vilanterol inhalation powder)

for oral inhalation use

What is TRELEGY ELLIPTA?

- TRELEGY ELLIPTA combines 3 medicines in 1 inhaler, an inhaled corticosteroid (ICS) medicine (fluticasone furoate), an anticholinergic medicine (umeclidinium), and a long-acting beta2-adrenergic agonist (LABA) medicine (vilanterol).
- ICS medicines such as fluticasone furoate help to decrease inflammation in the lungs. Inflammation in the lungs can lead to breathing problems.
- Anticholinergic medicines such as umeclidinium and LABA medicines such as vilanterol help the muscles around the airways in your lungs stay relaxed to prevent symptoms such as wheezing, cough, chest tightness, and shortness of breath. These symptoms can happen when the muscles around the airways tighten. This makes it hard to breathe.
- TRELEGY ELLIPTA is not used to relieve sudden breathing problems and will not replace a rescue inhaler.
- TRELEGY ELLIPTA is a prescription medicine used long term (chronic) to treat people with:
Chronic Obstructive Pulmonary Disease (COPD):
- TRELEGY ELLIPTA is a prescription medicine used to treat COPD. COPD is a chronic lung disease that includes chronic bronchitis, emphysema, or both.
- TRELEGY ELLIPTA is used to improve symptoms of COPD for better breathing and to reduce the number of flare-ups (the worsening of your COPD symptoms for several days).
Asthma:
- TRELEGY ELLIPTA is a prescription medicine used to prevent and control symptoms of asthma for better breathing and to prevent symptoms such as wheezing.
- TRELEGY ELLIPTA contains vilanterol. LABA medicines such as vilanterol when used alone increase the risk of hospitalizations and death from asthma problems. TRELEGY ELLIPTA contains an ICS, an anticholinergic, and a LABA. When an ICS and LABA are used together, there is not a significant increased risk in hospitalizations and death from asthma problems.

TRELEGY ELLIPTA should not be used in children younger than 18 years of age.

It is not known if TRELEGY ELLIPTA is safe and effective in children younger than 18 years of age.

Do not use TRELEGY ELLIPTA:

- to treat sudden, severe symptoms of COPD or asthma.
- if you have a severe allergy to milk proteins. Ask your healthcare provider if you are not sure.
- if you are allergic to fluticasone furoate, umeclidinium, vilanterol, or any of the ingredients in TRELEGY ELLIPTA. See the end of this Patient Information for a complete list of ingredients in TRELEGY ELLIPTA.

Before using TRELEGY ELLIPTA, tell your healthcare provider about all of your medical conditions, including if you:

- have heart problems.
- have high blood pressure.
- have seizures.
- have thyroid problems.
- have diabetes.
- have liver problems.
- have weak bones (osteoporosis).
- have an immune system problem.
- have eye problems such as glaucoma, increased pressure in your eye, cataracts, blurred vision, or other changes in vision. TRELEGY ELLIPTA may make your glaucoma worse.
- are allergic to milk proteins.
- have prostate or bladder problems, or problems passing urine. TRELEGY ELLIPTA may make these problems worse.
- have any type of viral, bacterial, parasitic, or fungal infection.
- are exposed to chickenpox or measles.
- are pregnant or plan to become pregnant. It is not known if TRELEGY ELLIPTA may harm your unborn baby.
- are breastfeeding or plan to breastfeed. It is not known if the medicines in TRELEGY ELLIPTA pass into your breast milk and if they can harm your baby.

Tell your healthcare provider about all the medicines you take, including prescription and over-the-counter medicines, vitamins, and herbal supplements. TRELEGY ELLIPTA and certain other medicines may interact with each other. This may cause serious side effects.

Especially tell your healthcare provider if you take:

- anticholinergics (including tiotropium, ipratropium, aclidinium)
- atropine
- other LABA (including salmeterol, formoterol, arformoterol, olodaterol, and indacaterol)
- antifungal or anti-HIV medicines.

Know the medicines you take. Keep a list of them to show your healthcare provider and pharmacist when you get a new medicine.

How should I use TRELEGY ELLIPTA?

Read the step-by-step instructions for using TRELEGY ELLIPTA at the end of this Patient Information.

- Do not use TRELEGY ELLIPTA unless your healthcare provider has taught you how to use the inhaler and you understand how to use it correctly.
- TRELEGY ELLIPTA comes in 2 different strengths. Your healthcare provider prescribed the strength that is best for you.
- Use TRELEGY ELLIPTA exactly as your healthcare provider tells you to use it. Do not use TRELEGY ELLIPTA more often than prescribed.
- Use 1 inhalation of TRELEGY ELLIPTA 1 time each day. Use TRELEGY ELLIPTA at the same time each day.
- If you miss a dose of TRELEGY ELLIPTA, take it as soon as you remember. Do not take more than 1 inhalation per day. Take your next dose at your usual time. Do not take 2 doses at 1 time.
- If you take too much TRELEGY ELLIPTA, call your healthcare provider or go to the nearest hospital emergency room right away if you have any unusual symptoms, such as worsening shortness of breath, chest pain, increased heart rate, or shakiness.
- Do not use other medicines that contain a LABA or an anticholinergic for any reason. Ask your healthcare provider or pharmacist if any of your other medicines are LABA or anticholinergic medicines.
- Do not stop using TRELEGY ELLIPTA unless told to do so by your healthcare provider because your symptoms might get worse. Your healthcare provider will change your medicines as needed.
- TRELEGY ELLIPTA does not relieve sudden symptoms of COPD or asthma and you should not take extra doses of TRELEGY ELLIPTA to relieve these sudden symptoms. Always have a rescue inhaler with you to treat sudden symptoms. If you do not have a rescue inhaler, call your healthcare provider to have one prescribed for you.
- Call your healthcare provider or get medical care right away if:
  - your breathing problems get worse.
  - you need to use your rescue inhaler more often than usual.
  - your rescue inhaler does not work as well to relieve your symptoms.

What are the possible side effects of TRELEGY ELLIPTA?

TRELEGY ELLIPTA can cause serious side effects, including:

- fungal infection in your mouth or throat (thrush). Rinse your mouth with water without swallowing after using TRELEGY ELLIPTA to help reduce your chance of getting thrush.
- pneumonia. People with COPD have a higher chance of getting pneumonia. TRELEGY ELLIPTA may increase the chance of getting pneumonia. Call your healthcare provider if you notice any of the following symptoms:

  - increase in mucus (sputum) production
  - change in mucus color
  - fever

- chills
- increased cough
- increased breathing problems

- weakened immune system and increased chance of getting infections (immunosuppression).
- reduced adrenal function (adrenal insufficiency). Adrenal insufficiency is a condition where the adrenal glands do not make enough steroid hormones. This can happen when you stop taking oral corticosteroid medicines (such as prednisone) and start taking a medicine containing an ICS (such as TRELEGY ELLIPTA). During this transition period, when your body is under stress from fever, trauma (such as a car accident), infection, surgery, or worse COPD or asthma symptoms, adrenal insufficiency can get worse and may cause death.
Symptoms of adrenal insufficiency include:

  - feeling tired
  - lack of energy
  - weakness

- nausea and vomiting
- low blood pressure (hypotension)

- sudden breathing problems immediately after inhaling your medicine. If you have sudden breathing problems immediately after inhaling your medicine, stop using TRELEGY ELLIPTA and call your healthcare provider right away.
- serious allergic reactions. Call your healthcare provider or get emergency medical care if you get any of the following symptoms of a serious allergic reaction:

  - rash
  - hives

- swelling of your face, mouth, and tongue
- breathing problems

- effects on heart.

  - increased blood pressure
  - a fast or irregular heartbeat, awareness of heartbeat

- chest pain

- effects on nervous system.

  - tremor

- nervousness

- bone thinning or weakness (osteoporosis).
- eye problems including glaucoma, increased pressure in your eye, cataracts, blurred vision, worsening of narrow-angle glaucoma, or other changes in vision. You should have regular eye exams while using TRELEGY ELLIPTA.
Acute narrow-angle glaucoma can cause permanent loss of vision if not treated. Symptoms of acute narrow-angle glaucoma may include:

  - eye pain or discomfort
  - nausea or vomiting
  - blurred vision

- seeing halos or bright colors around lights
- red eyes

If you have these symptoms, call your healthcare provider right away before taking another dose.
2. urinary retention. People who take TRELEGY ELLIPTA may develop new or worse urinary retention. Symptoms of urinary retention may include:

  - difficulty urinating
  - painful urination

- urinating frequently
- urination in a weak stream or drips

If you have these symptoms of urinary retention, stop taking TRELEGY ELLIPTA, and call your healthcare provider right away before taking another dose.
2. changes in laboratory blood values, including high levels of blood sugar (hyperglycemia) and low levels of potassium (hypokalemia).
3. slowed growth in children.

Common side effects of TRELEGY ELLIPTA include:

COPD:

- upper respiratory tract infection
- pneumonia
- bronchitis
- thrush in your mouth and throat. Rinse your mouth with water without swallowing after use to help prevent this.
- headache
- back pain
- joint pain
- flu
- inflammation of the sinuses

- runny nose and sore throat
- taste disturbance
- constipation
- painful and frequent urination
(signs of a urinary tract infection)
- nausea, vomiting, and diarrhea
- mouth and throat pain
- cough
- hoarseness

Asthma:

- runny nose and sore throat
- upper respiratory tract infection
- bronchitis
- respiratory tract infection
- inflammation of the sinuses

- respiratory tract infection
(signs of a urinary tract infection)
- flu
- headache
- back pain

These are not all the possible side effects of TRELEGY ELLIPTA.

Call your doctor for medical advice about side effects. You may report side effects to FDA at 1-800-FDA-1088.

How should I store TRELEGY ELLIPTA?

- Store TRELEGY ELLIPTA at room temperature between 68°F and 77°F (20°C and 25°C). Keep in a dry place away from heat and sunlight.
- Store TRELEGY ELLIPTA in the unopened tray and only open when ready for use.
- Safely throw away TRELEGY ELLIPTA in the trash 6 weeks after you open the tray or when the counter reads “0”, whichever comes first. Write the date you open the tray on the label on the inhaler.

Keep TRELEGY ELLIPTA and all medicines out of the reach of children.

General information about the safe and effective use of TRELEGY ELLIPTA.

Medicines are sometimes prescribed for purposes other than those listed in a Patient Information leaflet. Do not use TRELEGY ELLIPTA for a condition for which it was not prescribed. Do not give TRELEGY ELLIPTA to other people, even if they have the same symptoms that you have. It may harm them.

You can ask your healthcare provider or pharmacist for information about TRELEGY ELLIPTA that is written for health professionals.

What are the ingredients in TRELEGY ELLIPTA?

Active ingredients: fluticasone furoate, umeclidinium, vilanterol

Inactive ingredients: lactose monohydrate (contains milk proteins), magnesium stearate

For more information about TRELEGY ELLIPTA, call 1-888-825-5249 or visit our website at www.trelegy.com.

Trademarks are owned by or licensed to the GSK group of companies.

GlaxoSmithKline, Durham, NC 27701

©2022 GSK group of companies or its licensor.

TRL:7PIL

This Patient Information has been approved by the U.S. Food and Drug Administration Revised: December 2022

INSTRUCTIONS FOR USE

TRELEGY ELLIPTA (TREL-e-ge e-LIP-ta)

(fluticasone furoate, umeclidinium, and vilanterol inhalation powder)

for oral inhalation use

Read this before you start:

- If you open and close the cover without inhaling the medicine, you will lose the dose.
- The lost dose will be securely held inside the inhaler, but it will no longer be available to be inhaled.
- It is not possible to accidentally take a double dose or an extra dose in 1 inhalation.

Your TRELEGY ELLIPTA inhaler

How to use your inhaler

- TRELEGY ELLIPTA comes in a tray.
- Peel back the lid to open the tray. See Figure A.
- The tray contains a desiccant to reduce moisture. Do not eat or inhale. Throw it away in the household trash out of reach of children and pets. See Figure B.

Figure A

Figure B

Important Notes:

- Your inhaler contains 30 doses (14 doses if you have a sample or institutional pack).
- Each time you fully open the cover of the inhaler (you will hear a clicking sound), a dose is ready to be inhaled. This is shown by a decrease in the number on the counter.
- If you open and close the cover without inhaling the medicine, you will lose the dose. The lost dose will be held in the inhaler, but it will no longer be available to be inhaled. It is not possible to accidentally take a double dose or an extra dose in 1 inhalation.
- Do not open the cover of the inhaler until you are ready to use it. To avoid wasting doses after the inhaler is ready, do not close the cover until after you have inhaled the medicine.
- Write the “Tray opened” and “Discard” dates on the inhaler label. The “Discard” date is 6 weeks from the date you open the tray.

Check the counter. See Figure C.

Figure C

- Before the inhaler is used for the first time, the counter should show the number 30 (14 if you have a sample or institutional pack). This is the number of doses in the inhaler.
- Each time you open the cover, you prepare 1 dose of medicine.
- The counter counts down by 1 each time you open the cover.

Prepare your dose:

Wait to open the cover until you are ready to take your dose.

Figure D

Step 1. Open the cover of the inhaler. See Figure D.

- Slide the cover down to expose the mouthpiece. You should hear a “click.” The counter will count down by 1 number. You do not need to shake this kind of inhaler. Your inhaler is now ready to use.
- If the counter does not count down as you hear the click, the inhaler will not deliver the medicine. Call your healthcare provider or pharmacist if this happens.

Figure E

Step 2. Breathe out. See Figure E.

- While holding the inhaler away from your mouth, breathe out (exhale) fully. Do not breathe out into the mouthpiece.

Figure F

Step 3. Inhale your medicine. See Figure F.

- Put the mouthpiece between your lips, and close your lips firmly around it. Your lips should fit over the curved shape of the mouthpiece.
- Take one long, steady, deep breath in through your mouth. Do not breathe in through your nose.

Figure G

- Do not block the air vent with your fingers. See Figure G.

Figure H

- Remove the inhaler from your mouth and hold your breath for about 3 to 4 seconds (or as long as comfortable for you). See Figure H.

Figure I

Step 4. Breathe out slowly and gently. See Figure I.

- You may not taste or feel the medicine, even when you are using the inhaler correctly.
- Do not take another dose from the inhaler even if you do not feel or taste the medicine.

Figure J

Step 5. Close the inhaler. See Figure J.

- You can clean the mouthpiece if needed, using a dry tissue, before you close the cover. Routine cleaning is not required.
- Slide the cover up and over the mouthpiece as far as it will go.

Figure K

Step 6. Rinse your mouth. See Figure K.

- Rinse your mouth with water after you have used the inhaler and spit the water out. Do not swallow the water.

Important Note: When should you get a refill?

Figure L

- When you have fewer than 10 doses remaining in your inhaler, the left half of the counter shows red as a reminder to get a refill. See Figure L.
- After you have inhaled the last dose, the counter will show “0” and will be empty.
- Throw the empty inhaler away in your household trash out of reach of children and pets.

For more information about TRELEGY ELLIPTA or how to use your inhaler, call 1-888-825-5249 or visit our website at www.trelegy.com.

Trademarks are owned by or licensed to the GSK group of companies.

GlaxoSmithKline, Durham, NC 27701

©2022 GSK group of companies or its licensor.

TRL:4IFU

This Instructions for Use has been approved by the U.S. Food and Drug Administration Revised: December 2022

PACKAGE LABEL

PRINCIPAL DISPLAY PANEL

NDC 0173-0887-10

TRELEGY ELLIPTA

(fluticasone furoate, umeclidinium, and vilanterol inhalation powder)

100 mcg/62.5 mcg/25 mcg

Rx Only

FOR ORAL INHALATION ONLY

TRELEGY ELLIPTA contains 2 foils strips of 30 blisters each. Each blister on one strip contains 100 mcg of fluticasone furoate and lactose monohydrate. Each blister on the other strip contains 62.5 mcg of umeclidinium, 25 mcg of vilanterol, magnesium stearate, and lactose monohydrate.

1 ELLIPTA Inhaler containing 30 doses (60 blisters total)

GSK

Made in UK

©2025 GSK group of companies or its licensor.

62000000099742 Rev. 4/25

PACKAGE LABEL

PRINCIPAL DISPLAY PANEL

NDC 0173-0893-10

TRELEGY ELLIPTA

(fluticasone furoate, umeclidinium, and vilanterol inhalation powder)

200 mcg/62.5 mcg/25 mcg

Rx Only

FOR ORAL INHALATION ONLY

TRELEGY ELLIPTA contains 2 foils strips of 30 blisters each. Each blister on one strip contains 200 mcg of fluticasone furoate and lactose monohydrate. Each blister on the other strip contains 62.5 mcg of umeclidinium, 25 mcg of vilanterol, magnesium stearate, and lactose monohydrate.

1 ELLIPTA Inhaler containing 30 doses (60 blisters total)

GSK

Made in UK

©2025 GSK group of companies or its licensor.

62000000099735 Rev. 4/25